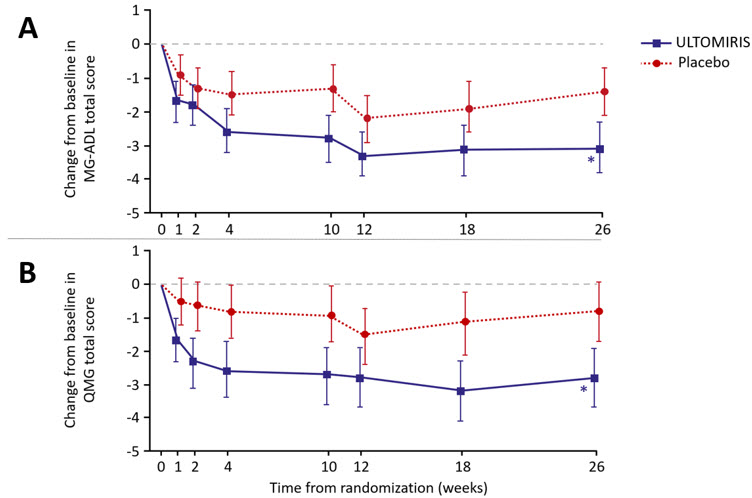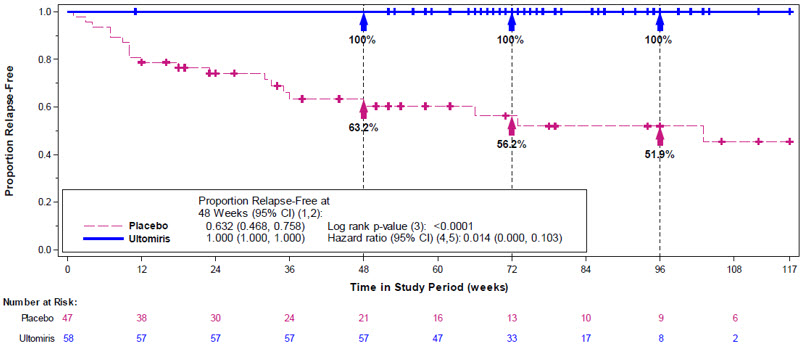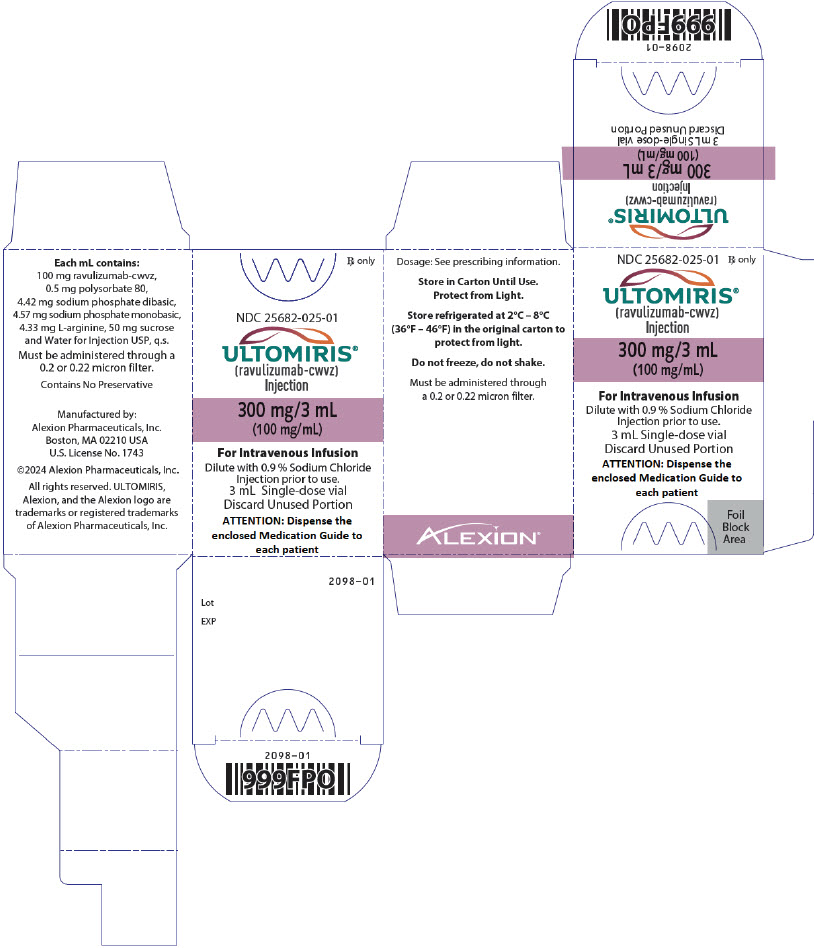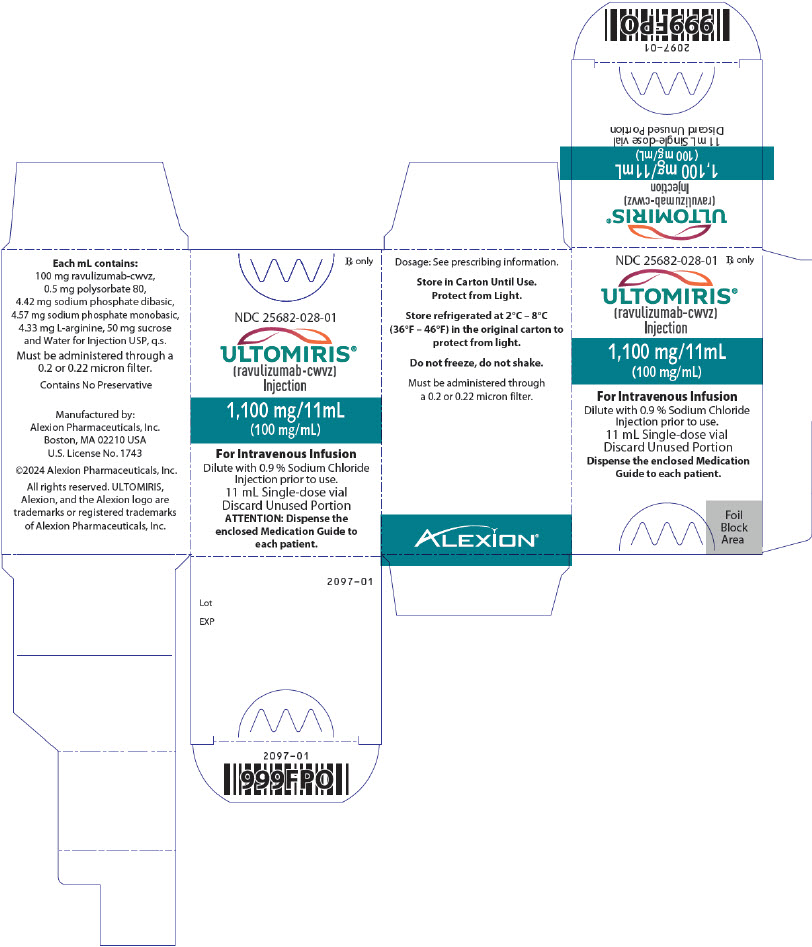 DRUG LABEL: Ultomiris
NDC: 25682-022 | Form: SOLUTION, CONCENTRATE
Manufacturer: Alexion Pharmaceuticals Inc.
Category: prescription | Type: HUMAN PRESCRIPTION DRUG LABEL
Date: 20251009

ACTIVE INGREDIENTS: ravulizumab 300 mg/30 mL

HIGHLIGHTS OF PRESCRIBING INFORMATION

These highlights do not include all the information needed to use ULTOMIRIS safely and effectively. See full prescribing information for ULTOMIRIS.
ULTOMIRIS® (ravulizumab-cwvz) injection, for intravenous use
Initial U.S. Approval: 2018

WARNING: SERIOUS MENINGOCOCCAL INFECTIONS

See full prescribing information for complete boxed warning.

ULTOMIRIS increases the risk of serious and life-threatening infections caused by Neisseria meningitidis.

- Complete or update meningococcal vaccination at least 2 weeks prior to the first dose of ULTOMIRIS, unless the risks of delaying ULTOMIRIS outweigh the risks of developing a serious infection. Comply with the most current Advisory Committee on Immunization Practices (ACIP) recommendations for meningococcal vaccination in patients receiving a complement inhibitor. (5.1)
- Patients receiving ULTOMIRIS are at increased risk for invasive disease caused by N. meningitidis, even if they develop antibodies following vaccination. Monitor patients for early signs and symptoms of meningococcal infections and evaluate immediately if infection is suspected. (5.1)

ULTOMIRIS is available only through a restricted program called ULTOMIRIS and SOLIRIS REMS. (5.2)

RECENT MAJOR CHANGES

Dosage and Administration (2.2, 2.3, 2.5) | 09/2025
Dosage Forms and Strengths (3) | 09/2025

1 INDICATIONS AND USAGE

ULTOMIRIS is a complement inhibitor indicated for:

- the treatment of adult and pediatric patients one month of age and older with paroxysmal nocturnal hemoglobinuria (PNH). (1.1)
- the treatment of adult and pediatric patients one month of age and older with atypical hemolytic uremic syndrome (aHUS) to inhibit complement-mediated thrombotic microangiopathy (TMA). (1.2)
  Limitations of Use:
  ULTOMIRIS is not indicated for the treatment of patients with Shiga toxin E. coli related hemolytic uremic syndrome (STEC-HUS).
- the treatment of adult patients with generalized myasthenia gravis (gMG) who are anti-acetylcholine receptor (AChR) antibody-positive. (1.3)
- the treatment of adult patients with neuromyelitis optica spectrum disorder (NMOSD) who are anti-aquaporin-4 (AQP4) antibody-positive. (1.4)

2 DOSAGE AND ADMINISTRATION

- See Full Prescribing Information for instructions on dosage, preparation, and administration. (2.1, 2.2, 2.3, 2.4, 2.5)
- Dilute ULTOMIRIS before use. (2.5)
- Only administer as an intravenous infusion through a 0.2 or 0.22 micron filter. (2.5)

3 DOSAGE FORMS AND STRENGTHS

Injection:

- 300 mg/3 mL (100 mg/mL) solution in a single-dose vial. (3)
- 1,100 mg/11 mL (100 mg/mL) solution in a single-dose vial. (3)

4 CONTRAINDICATIONS

ULTOMIRIS is contraindicated for initiation in patients with unresolved serious Neisseria meningitidis infection. (4)

5 WARNINGS AND PRECAUTIONS

- Other Infections: Use caution when administering ULTOMIRIS to patients with any other systemic infection. (5.3)
- Infusion-Related Reactions: Monitor during infusion, interrupt for reactions, and institute appropriate supportive measures. (5.6)

6 ADVERSE REACTIONS

Most common adverse reactions in patients with PNH (incidence ≥ 10%) were upper respiratory tract infection and headache. (6.1)

Most common adverse reactions in patients with aHUS (incidence ≥ 20%) were upper respiratory tract infection, diarrhea, nausea, vomiting, headache, hypertension, and pyrexia. (6.1)

Most common adverse reactions in adult patients with gMG (incidence ≥ 10%) were diarrhea and upper respiratory tract infection. (6.1)

Most common adverse reactions in adult patients with NMOSD (incidence ≥ 10%) were COVID-19, headache, back pain, arthralgia, and urinary tract infection. (6.1)

To report SUSPECTED ADVERSE REACTIONS, contact Alexion Pharmaceuticals, Inc. at 1-844-259-6783 or FDA at 1-800-FDA-1088 or www.fda.gov/medwatch.

7 DRUG INTERACTIONS

- Plasma Exchange, Plasmapheresis, or Intravenous Immunoglobulins: concomitant use requires supplemental dose of ULTOMIRIS. (7.1)
- Neonatal Fc Receptor Blockers (FcRn): Closely monitor for reduced effectiveness of ULTOMIRIS. (7.2)

FULL PRESCRIBING INFORMATION

WARNING: SERIOUS MENINGOCOCCAL INFECTIONS

ULTOMIRIS, a complement inhibitor, increases the risk of serious infections caused by Neisseria meningitidis [see Warnings and Precautions (5.1)]. Life-threatening and fatal meningococcal infections have occurred in patients treated with complement inhibitors. These infections may become rapidly life-threatening or fatal if not recognized and treated early.

- Complete or update vaccination for meningococcal bacteria (for serogroups A, C, W, Y, and B) at least 2 weeks prior to the first dose of ULTOMIRIS, unless the risks of delaying therapy with ULTOMIRIS outweigh the risk of developing a serious infection. Comply with the most current Advisory Committee on Immunization Practices (ACIP) recommendations for vaccinations against meningococcal bacteria in patients receiving a complement inhibitor. See Warnings and Precautions (5.1) for additional guidance on the management of the risk of serious infections caused by meningococcal bacteria.
- Patients receiving ULTOMIRIS are at increased risk for invasive disease caused by Neisseria meningitidis, even if they develop antibodies following vaccination. Monitor patients for early signs and symptoms of serious meningococcal infections and evaluate immediately if infection is suspected.

Because of the risk of serious meningococcal infections, ULTOMIRIS is available only through a restricted program under a Risk Evaluation and Mitigation Strategy (REMS) called ULTOMIRIS and SOLIRIS REMS [see Warnings and Precautions (5.2)].

1 INDICATIONS AND USAGE

1.1 Paroxysmal Nocturnal Hemoglobinuria

ULTOMIRIS is indicated for the treatment of adult and pediatric patients one month of age and older with paroxysmal nocturnal hemoglobinuria (PNH).

1.2 Atypical Hemolytic Uremic Syndrome

ULTOMIRIS is indicated for the treatment of adult and pediatric patients one month of age and older with atypical hemolytic uremic syndrome (aHUS) to inhibit complement-mediated thrombotic microangiopathy (TMA).

Limitations of Use:

ULTOMIRIS is not indicated for the treatment of patients with Shiga toxin E. coli related hemolytic uremic syndrome (STEC-HUS).

1.3 Generalized Myasthenia Gravis

ULTOMIRIS is indicated for the treatment of adult patients with generalized myasthenia gravis (gMG) who are anti-acetylcholine receptor (AChR) antibody-positive.

1.4 Neuromyelitis Optica Spectrum Disorder

ULTOMIRIS is indicated for the treatment of adult patients with neuromyelitis optica spectrum disorder (NMOSD) who are anti-aquaporin-4 (AQP4) antibody-positive.

2 DOSAGE AND ADMINISTRATION

2.1 Important Dosage Information

ULTOMIRIS is intended to be administered only as an intravenous infusion in adult or pediatric patients one month of age and older.

2.2 Recommended Vaccination and Prophylaxis for Meningococcal Infection

Vaccinate patients against meningococcal infection (serogroups A, C, W, Y and B) according to current ACIP recommendations at least 2 weeks prior to initiation of ULTOMIRIS [see Warnings and Precautions (5.1)].

If urgent ULTOMIRIS therapy is indicated in a patient who is not up to date with meningococcal vaccines according to ACIP recommendations, provide the patient with antibacterial drug prophylaxis and administer these vaccines as soon as possible.

Healthcare providers who prescribe ULTOMIRIS must enroll in the ULTOMIRIS and SOLIRIS REMS [see Warnings and Precautions (5.2)].

2.3 Recommended Dosage for Intravenous Administration in Adult and Pediatric Patients with PNH or aHUS, and in Adult Patients with gMG or NMOSD

The recommended intravenous (IV) ULTOMIRIS loading and maintenance dosing in adult and pediatric patients, one month of age or older weighing 5 kg or greater, with PNH or aHUS, or in adult patients with gMG or NMOSD weighing 40 kg or greater, is based on the patient's body weight, as shown in Table 1, with maintenance doses administered every 4 or 8 weeks, starting 2 weeks after loading dose.

The IV dosing schedule is allowed to occasionally vary within 7 days of the scheduled infusion day (except for the first maintenance dose of ULTOMIRIS); but subsequent doses should be administered according to the original schedule.

Following a missed IV ULTOMIRIS dose, the patient should contact their health care provider immediately.

Table 1: IV Administration of ULTOMIRIS Weight-Based Dosing Regimen – PNH, aHUS, gMG, or NMOSD [See Table 4 and Table 5 for selection of the proper total volume and maximum infusion rate [see Dosage and Administration (2.5)]]
Indications | Body Weight Range (kg) | Loading Dose (mg) [See Table 2 for ULTOMIRIS treatment initiation instruction and timing of loading dose and maintenance dose] | Maintenance Dose (mg) and Dosing Interval
PNH or aHUS | 5 to less than 10 | 600 | 300 | Every 4 weeks
PNH or aHUS | 10 to less than 20 | 600 | 600 | Every 4 weeks
PNH or aHUS | 20 to less than 30 | 900 | 2,100 | Every 8 weeks
PNH or aHUS | 30 to less than 40 | 1,200 | 2,700 | Every 8 weeks
PNH, aHUS, gMG, or NMOSD | 40 to less than 60 | 2,400 | 3,000 | Every 8 weeks
PNH, aHUS, gMG, or NMOSD | 60 to less than 100 | 2,700 | 3,300 | Every 8 weeks
PNH, aHUS, gMG, or NMOSD | 100 or greater | 3,000 | 3,600 | Every 8 weeks

Refer to Table 2 for treatment initiation instructions in patients who are complement inhibitor treatment-naïve or switching treatment from eculizumab.

Table 2: IV Administration of ULTOMIRIS Treatment Initiation Instructions – PNH, aHUS, gMG, or NMOSD
Population | Weight-based ULTOMIRIS Loading Dose | Time of First ULTOMIRIS Weight-based Maintenance Dose
Not currently on ULTOMIRIS or eculizumab treatment | At treatment start | 2 weeks after ULTOMIRIS loading dose
Currently treated with eculizumab | At time of next scheduled eculizumab dose | 2 weeks after ULTOMIRIS loading dose

2.4 Dosing Considerations

Supplemental Dose of ULTOMIRIS

Plasma exchange (PE), plasmapheresis (PP), and intravenous immunoglobulin (IVIg) have been shown to reduce ULTOMIRIS serum levels. A supplemental dose of ULTOMIRIS is required in the setting of PE, PP, or IVIg (Table 3).

Table 3: Supplemental Dose of ULTOMIRIS after PE, PP, or IVIg [See Table 6 for selection of the proper total volume and maximum infusion rate [see Dosage and Administration (2.5)]]
Body Weight Range (kg) | Most Recent ULTOMIRIS Dose (mg) | Supplemental Dose (mg) following each PE or PP Intervention | Supplemental Dose (mg) following Completion of an IVIg Cycle
40 to less than 60 | 2,400 | 1,200 | 600
40 to less than 60 | 3,000 | 1,500 | 600
60 to less than 100 | 2,700 | 1,500 | 600
60 to less than 100 | 3,300 | 1,800 | 600
100 or greater | 3,000 | 1,500 | 600
100 or greater | 3,600 | 1,800 | 600
Timing of ULTOMIRIS Supplemental Dose |  | Within 4 hours following each PE or PP intervention | Within 4 hours following completion of an IVIg cycle
Abbreviations: IVIg = intravenous immunoglobulin; PE = plasma exchange; PP = plasmapheresis

2.5 Preparation and Administration

Preparation of ULTOMIRIS Vials for Intravenous Administration

Each vial of ULTOMIRIS is intended for single-dose only.

ULTOMIRIS vials are for intravenous administration by a healthcare provider and are intended for intravenous administration only.

Dilute before use.

Use aseptic technique to prepare ULTOMIRIS as follows:

1. The number of vials to be diluted is determined based on the individual patient's weight and the prescribed dose [see Dosage and Administration (2.3)].
2. Prior to dilution, visually inspect the solution in the vials; the solution should be free of any particulate matter or precipitation. Do not use if there is evidence of particulate matter or precipitation.
3. Withdraw the calculated volume of ULTOMIRIS from the appropriate number of vials and dilute in an infusion bag using 0.9% Sodium Chloride Injection, USP to a final concentration of 50 mg/mL.

The product should be mixed gently. Do not shake. Protect from light. Do not freeze.

Refer to Table 4 (loading doses), Table 5 (maintenance doses), and Table 6 (supplemental doses) for IV preparation and minimum infusion duration.

4. Administer the prepared solution immediately following preparation.
5. If the diluted ULTOMIRIS infusion solution is not used immediately, storage under refrigeration at 2°C - 8°C (36°F - 46°F) must not exceed 24 hours taking into account the expected infusion time. Once removed from refrigeration, administer the diluted ULTOMIRIS infusion solution within 4 hours.

Intravenous Administration of ULTOMIRIS (Healthcare Providers)

Only administer as an intravenous infusion through a 0.2 or 0.22 micron filter.

Dilute ULTOMIRIS to a final concentration of 50 mg/mL.

Prior to administration, allow the admixture to adjust to room temperature (18°C - 25°C, 64°F - 77°F). Do not heat the admixture in a microwave or with any heat source other than ambient air temperature.

Parenteral drug products should be inspected visually for particulate matter and discoloration prior to administration, whenever solution and container permit.

After administration of ULTOMIRIS, flush the entire line with 0.9% Sodium Chloride Injection, USP.

Table 4: Loading Dose Reference Table for ULTOMIRIS
Body Weight Range (kg) [Body weight at time of treatment.] | Loading Dose (mg) | ULTOMIRIS Volume (mL) | Volume of NaCl Diluent [Dilute ULTOMIRIS only using 0.9% Sodium Chloride Injection, USP.] (mL) | Total Volume (mL) | Minimum Infusion Time (hr) | Maximum Infusion Rate (mL/hr)
5 to less than 10 [For PNH and aHUS indications only.] | 600 | 6 | 6 | 12 | 1.4 | 9
10 to less than 20 | 600 | 6 | 6 | 12 | 0.8 | 15
20 to less than 30 | 900 | 9 | 9 | 18 | 0.6 | 30
30 to less than 40 | 1,200 | 12 | 12 | 24 | 0.5 | 48
40 to less than 60 | 2,400 | 24 | 24 | 48 | 0.8 | 60
60 to less than 100 | 2,700 | 27 | 27 | 54 | 0.6 | 90
100 or greater | 3,000 | 30 | 30 | 60 | 0.4 | 150

Table 5: Maintenance Dose Reference Table for ULTOMIRIS
Body Weight Range (kg) [Body weight at time of treatment.] | Maintenance Dose (mg) | ULTOMIRIS Volume (mL) | Volume of NaCl Diluent [Dilute ULTOMIRIS only using 0.9% Sodium Chloride Injection, USP.] (mL) | Total Volume (mL) | Minimum Infusion Time (hr) | Maximum Infusion Rate (mL/hr)
5 to less than 10 [For PNH and aHUS indications only.] | 300 | 3 | 3 | 6 | 0.8 | 8
10 to less than 20 | 600 | 6 | 6 | 12 | 0.8 | 15
20 to less than 30 | 2,100 | 21 | 21 | 42 | 1.3 | 33
30 to less than 40 | 2,700 | 27 | 27 | 54 | 1.1 | 50
40 to less than 60 | 3,000 | 30 | 30 | 60 | 0.9 | 67
60 to less than 100 | 3,300 | 33 | 33 | 66 | 0.7 | 95
100 or greater | 3,600 | 36 | 36 | 72 | 0.5 | 144

Table 6: Supplemental Dose Reference Table for ULTOMIRIS
Body Weight Range (kg) [Body weight at time of treatment.] | Supplemental Dose (mg) | ULTOMIRIS Volume (mL) | Volume of NaCl Diluent [Dilute ULTOMIRIS only using 0.9% Sodium Chloride Injection, USP.] (mL) | Total Volume (mL) | Minimum Infusion Time (hr) | Maximum Infusion Rate (mL/hr)
40 to less than 60 | 600 | 6 | 6 | 12 | 0.25 | 48
40 to less than 60 | 1,200 | 12 | 12 | 24 | 0.42 | 57
40 to less than 60 | 1,500 | 15 | 15 | 30 | 0.5 | 60
60 to less than 100 | 600 | 6 | 6 | 12 | 0.20 | 60
60 to less than 100 | 1,500 | 15 | 15 | 30 | 0.36 | 83
60 to less than 100 | 1,800 | 18 | 18 | 36 | 0.42 | 86
100 or greater | 600 | 6 | 6 | 12 | 0.17 | 71
100 or greater | 1,500 | 15 | 15 | 30 | 0.25 | 120
100 or greater | 1,800 | 18 | 18 | 36 | 0.28 | 129
Note: Refer to Table 3 for selection of ravulizumab supplemental dose

If an adverse reaction occurs during the administration of ULTOMIRIS, the infusion may be slowed or stopped at the discretion of the physician. Monitor the patient for at least 1 hour following completion of the infusion for signs or symptoms of an infusion-related reaction.

3 DOSAGE FORMS AND STRENGTHS

Injection: 300 mg/3 mL or 1,100 mg/11 mL (100 mg/mL) as a translucent, clear to yellowish color solution in a single-dose vial.

4 CONTRAINDICATIONS

ULTOMIRIS is contraindicated for initiation in patients with unresolved serious Neisseria meningitidis infection [see Warnings and Precautions (5.1)].

5 WARNINGS AND PRECAUTIONS

5.1 Serious Meningococcal Infections

ULTOMIRIS, a complement inhibitor, increases a patient's susceptibility to serious, life-threatening, or fatal infections caused by meningococcal bacteria (septicemia and/or meningitis) in any serogroup, including non-groupable strains. Life-threatening and fatal meningococcal infections have occurred in both vaccinated and unvaccinated patients treated with complement inhibitors. The initiation of ULTOMIRIS treatment is contraindicated in patients with unresolved serious Neisseria meningitidis infection.

Complete or update meningococcal vaccination (for serogroups A, C, W, Y and B) at least 2 weeks prior to administration of the first dose of ULTOMIRIS, according to current ACIP recommendations for patients receiving a complement inhibitor. Revaccinate patients in accordance with ACIP recommendations considering the duration of ULTOMIRIS therapy. Note that ACIP recommends an administration schedule in patients receiving complement inhibitors that differs from the administration schedule in the vaccine prescribing information. If urgent ULTOMIRIS therapy is indicated in a patient who is not up to date with meningococcal vaccines according to ACIP recommendations, provide the patient with antibacterial drug prophylaxis and administer meningococcal vaccines as soon as possible. Various durations and regimens of antibacterial drug prophylaxis have been considered, but the optimal durations and drug regimens for prophylaxis and their efficacy have not been studied in unvaccinated or vaccinated patients receiving complement inhibitors, including ULTOMIRIS. The benefits and risks of treatment with ULTOMIRIS, as well as the benefits and risks of antibacterial drug prophylaxis in unvaccinated or vaccinated patients, must be considered against the known risks for serious infections caused by Neisseria meningitidis.

Vaccination does not eliminate the risk of meningococcal infections, despite development of antibodies following vaccination.

Closely monitor patients for early signs and symptoms of meningococcal infection and evaluate patients immediately if infection is suspected. Inform patients of these signs and symptoms and instruct patients to seek immediate medical care if these signs and symptoms occur. Promptly treat known infections. Meningococcal infection may become rapidly life-threatening or fatal if not recognized and treated early. Consider interruption of ULTOMIRIS in patients who are undergoing treatment for serious meningococcal infection, depending on the risks of interrupting treatment in the disease being treated.

ULTOMIRIS is available only through a restricted program under a REMS [see Warnings and Precautions (5.2)].

5.2 ULTOMIRIS and SOLIRIS REMS

ULTOMIRIS is available only through a restricted program under a REMS called ULTOMIRIS and SOLIRIS REMS, because of the risk of serious meningococcal infections [see Warnings and Precautions (5.1)].

Notable requirements of the ULTOMIRIS and SOLIRIS REMS include the following:

- Prescribers must enroll in the REMS.
- Prescribers must counsel patients about the risk of serious meningococcal infection.
- Prescribers must provide the patients with the REMS educational materials.
- Prescribers must assess patient vaccination status for meningococcal vaccines (against serogroups A, C, W, Y, and B) and vaccinate if needed according to current ACIP recommendations two weeks prior to the first dose of ULTOMIRIS.
- Prescribers must provide a prescription for antibacterial drug prophylaxis if treatment must be started urgently and the patient is not up to date with meningococcal vaccines according to current ACIP recommendations at least two weeks prior to the first dose of ULTOMIRIS.
- Healthcare settings and pharmacies that dispense ULTOMIRIS must be certified in the REMS and must verify prescribers are certified.
- Patients must receive counseling from the prescriber about the need to receive meningococcal vaccines per ACIP recommendations, the need to take antibiotics as directed by the prescriber, and the signs and symptoms of meningococcal infection.
- Patients must be instructed to carry the Patient Safety Card with them at all times during and for 8 months following treatment with ULTOMIRIS.

Further information is available at www.UltSolREMS.com or 1-888-765-4747.

5.3 Other Infections

Serious infections with Neisseria species (other than Neisseria meningitidis), including disseminated gonococcal infections, have been reported.

ULTOMIRIS blocks terminal complement activation; therefore, patients may have increased susceptibility to infections, especially with encapsulated bacteria, such as infections caused by Neisseria meningitidis but also Streptococcus pneumoniae, Haemophilus influenzae, and to a lesser extent, Neisseria gonorrhoeae. Children treated with ULTOMIRIS may be at increased risk of developing serious infections due to Streptococcus pneumoniae and Haemophilus influenzae type b (Hib). Administer vaccinations for the prevention of Streptococcus pneumoniae and Haemophilus influenzae type b (Hib) infections according to ACIP recommendations. Patients receiving ULTOMIRIS are at increased risk for infections due to these organisms, even if they develop antibodies following vaccination.

5.4 Monitoring Disease Manifestations after ULTOMIRIS Discontinuation

Treatment Discontinuation for PNH

After discontinuing treatment with ULTOMIRIS, closely monitor for signs and symptoms of hemolysis, identified by elevated lactate dehydrogenase (LDH) along with sudden decrease in PNH clone size or hemoglobin, or reappearance of symptoms such as fatigue, hemoglobinuria, abdominal pain, shortness of breath (dyspnea), major adverse vascular event (including thrombosis), dysphagia, or erectile dysfunction. Monitor any patient who discontinues ULTOMIRIS for at least 16 weeks to detect hemolysis and other reactions. If signs and symptoms of hemolysis occur after discontinuation, including elevated LDH, consider restarting treatment with ULTOMIRIS.

Treatment Discontinuation for aHUS

ULTOMIRIS treatment of aHUS should be a minimum duration of 6 months. Due to heterogeneous nature of aHUS events and patient-specific risk factors, treatment duration beyond the initial 6 months should be individualized.

There are no specific data on ULTOMIRIS discontinuation.

After discontinuing treatment with ULTOMIRIS, patients should be monitored for clinical symptoms and laboratory signs of TMA complications for at least 12 months.

TMA complications post-discontinuation can be identified if any of the following is observed:

- Clinical symptoms of TMA include changes in mental status, seizures, angina, dyspnea, thrombosis or increasing blood pressure.
- In addition, at least two of the following laboratory signs observed concurrently and results should be confirmed by a second measurement 28 days apart with no interruption:
  - a decrease in platelet count of 25% or more as compared to either baseline or to peak platelet count during ULTOMIRIS treatment;
  - an increase in serum creatinine of 25% or more as compared to baseline or to nadir during ULTOMIRIS treatment;
  - an increase in serum LDH of 25% or more as compared to baseline or to nadir during ULTOMIRIS treatment.

If TMA complications occur after ULTOMIRIS discontinuation, consider reinitiation of ULTOMIRIS treatment or appropriate organ-specific supportive measures.

5.5 Thromboembolic Event Management

The effect of withdrawal of anticoagulant therapy during ULTOMIRIS treatment has not been established. Therefore, treatment with ULTOMIRIS should not alter anticoagulant management.

5.6 Infusion-Related Reactions

Administration of ULTOMIRIS may result in systemic infusion-related reactions, including anaphylaxis [see Adverse Reactions (6.2)] and hypersensitivity reactions. In clinical trials, infusion-related reactions occurred in approximately 1 to 7% of patients treated with ULTOMIRIS [see Adverse Reactions (6.1)]. These events included lower back pain, abdominal pain, muscle spasms, drop in blood pressure, elevation in blood pressure, rigors, limb discomfort, drug hypersensitivity (allergic reaction), and dysgeusia (bad taste). These reactions did not require discontinuation of ULTOMIRIS. If signs of cardiovascular instability or respiratory compromise occur, interrupt ULTOMIRIS infusion and institute appropriate supportive measures.

6 ADVERSE REACTIONS

The following clinically significant adverse reactions are discussed in greater detail in other sections of the labeling:

- Serious Meningococcal Infections [see Warnings and Precautions (5.1)]
- Other Infections [see Warnings and Precautions (5.3)]
- Infusion-Related Reactions [see Warnings and Precautions (5.6)]

6.1 Clinical Trial Experience

Because clinical trials are conducted under widely varying conditions, adverse reaction rates observed in the clinical trials of a drug cannot be directly compared to rates in the clinical trials of another drug and may not reflect the rates observed in practice.

Paroxysmal Nocturnal Hemoglobinuria (PNH)

Adult Population with PNH Treated with ULTOMIRIS

The data described below reflect exposure of 441 adult patients with PNH in Phase 3 studies who received ULTOMIRIS (n = 222) or eculizumab (n = 219) at the recommended dosing regimens with median treatment duration of 6 months for ULTOMIRIS and 6 months for eculizumab. The most frequent adverse reactions (≥ 10%) with ULTOMIRIS were upper respiratory tract infection and headache. Table 7 describes adverse reactions that occurred at a rate of 5% or more among patients treated with ULTOMIRIS in PNH studies.

Serious adverse reactions were reported in 15 (6.8%) patients with PNH receiving ULTOMIRIS. The serious adverse reactions in patients treated with ULTOMIRIS included hyperthermia and pyrexia. No serious adverse reaction was reported in more than 1 patient treated with ULTOMIRIS.

One fatal case of sepsis was identified in a patient treated with ULTOMIRIS.

Table 7: Adverse Reactions Reported in 5% or More of ULTOMIRIS-Treated Patients in Complement Inhibitor-Naïve and Eculizumab-Experienced Adult Patients with PNH
Body System Adverse Reaction | Number of Patients
Body System Adverse Reaction | ULTOMIRIS (N=222) n (%) | Eculizumab (N=219) n (%)
Gastrointestinal disorders
Diarrhea | 19 (9) | 12 (5)
Nausea | 19 (9) | 19 (9)
Abdominal pain | 13 (6) | 16 (7)
General disorders and administration site conditions
Pyrexia | 15 (7) | 18 (8)
Infections and infestations
Upper respiratory tract infection [Grouped term includes: nasopharyngitis, upper respiratory tract infection, oropharyngeal pain, viral upper respiratory tract infection, rhinitis, respiratory tract infection, rhinorrhea, pharyngitis, and upper respiratory tract inflammation] | 86 (39) | 86 (39)
Musculoskeletal and connective tissue disorders
Pain in extremity | 14 (6) | 11 (5)
Arthralgia | 11 (5) | 12 (5)
Nervous system disorders
Headache | 71 (32) | 57 (26)
Dizziness | 12 (5) | 14 (6)

Clinically relevant adverse reactions in 1% of patients include infusion-related reactions.

Pediatric Population with PNH Treated with ULTOMIRIS

In pediatric patients with PNH (aged 9 to 17 years old) included in the pediatric PNH Phase 3 study, the safety profile appeared similar to that observed in adult patients with PNH and in pediatric and adult patients with aHUS. The most common adverse reactions (> 20%) were upper respiratory tract infection, anemia, abdominal pain, and headache. Table 8 describes the adverse reactions that occurred at a rate of 10% or more among pediatric patients treated with ULTOMIRIS in Study ALXN1210-PNH-304.

Table 8: Adverse Reactions Reported in 10% or More of ULTOMIRIS-Treated Pediatric Patients with PNH in Study ALXN1210-PNH-304
Body System Adverse Reaction | Treatment Naïve (N=5) | Eculizumab Experienced (N=8) | Total (N=13)
Body System Adverse Reaction | n (%) | n (%) | n (%)
Body System Adverse Reaction | Blood and lymphatic system disorders
Anemia [Grouped term includes: anemia and iron deficiency anemia] | 1 (20) | 2 (25) | 3 (23)
Gastrointestinal disorders
Abdominal pain | 0 (0) | 3 (38) | 3 (23)
Constipation | 0 (0) | 2 (25) | 2 (15)
General disorders and administration site conditions
Pyrexia | 1 (20) | 1 (13) | 2 (15)
Infections and infestations
Upper Respiratory tract infection [Grouped term includes: nasopharyngitis, upper respiratory tract infection, oropharyngeal pain, and viral upper respiratory tract infection] | 1 (20) | 6 (75) | 7 (54)
Musculoskeletal and connective tissue disorders
Pain in extremity | 0 (0) | 2 (25) | 2 (15)
Nervous system disorders
Headache | 1 (20) | 2 (25) | 3 (23)

Atypical Hemolytic Uremic Syndrome (aHUS)

The data described below reflect exposure of 58 adult and 16 pediatric patients with aHUS in single-arm trials who received ULTOMIRIS at the recommended dose and schedule. The most frequent adverse reactions reported in ≥ 20% of patients treated with ULTOMIRIS were upper respiratory tract infection, diarrhea, nausea, vomiting, headache, hypertension, and pyrexia. Table 9, Table 10 and Table 11 describe adverse reactions that occurred at a rate of 10% or more among patients treated with ULTOMIRIS in aHUS studies. Serious adverse reactions were reported in 42 (57%) patients with aHUS receiving ULTOMIRIS. The most frequent serious adverse reactions reported in more than 2 patients (2.7%) treated with ULTOMIRIS were hypertension, pneumonia, and abdominal pain. Four patients died during the ALXN1210-aHUS-311 study. The cause of death was sepsis in 2 patients and intracranial hemorrhage in 1 patient. The fourth patient, who was excluded from the trial after a diagnosis of STEC-HUS, died due to pretreatment cerebral arterial thrombosis.

Table 9: Adverse Reactions Reported in ≥ 10% of ULTOMIRIS-Treated Patients with aHUS in Study ALXN1210-aHUS-311
Body System Adverse Reaction | ALXN1210-aHUS-311 (N=58)
Body System Adverse Reaction | All Grades [Graded per CTCAE v5.0.] (n=53) n (%) | ≥ Grade 3 (n=14) n (%)
Blood and lymphatic system disorders
Anemia | 8 (14) | 0 (0)
Gastrointestinal disorders
Diarrhea | 18 (31) | 2 (3)
Nausea | 15 (26) | 2 (3)
Vomiting | 15 (26) | 2 (3)
Constipation | 8 (14) | 1 (2)
Abdominal pain | 7 (12) | 1 (2)
General disorders and administration site conditions
Pyrexia | 11 (19) | 1 (2)
Edema peripheral | 10 (17) | 0 (0)
Fatigue | 8 (14) | 0 (0)
Infections and infestations
Upper respiratory tract infection [Grouped term includes nasopharyngitis, pharyngitis, upper respiratory tract infection, rhinitis, viral upper respiratory tract infection, rhinovirus infection, viral pharyngitis, rhinorrhea, and oropharyngeal pain.] | 15 (26) | 0 (0)
Urinary tract infection | 10 (17) | 5 (9)
Gastrointestinal infection [Grouped term includes gastroenteritis, gastrointestinal infection, enterocolitis infectious, infectious colitis, and enterocolitis.] | 8 (14) | 2 (3)
Metabolism and nutrition disorders
Hypokalemia | 6 (10) | 1 (2)
Musculoskeletal and connective tissue disorders
Arthralgia | 13 (22) | 0 (0)
Back pain | 7 (12) | 1 (2)
Muscle spasms | 6 (10) | 0 (0)
Pain in extremity | 6 (10) | 0 (0)
Nervous system disorders
Headache | 23 (40) | 1 (2)
Psychiatric disorders
Anxiety | 8 (14) | 1 (2)
Respiratory, thoracic and mediastinal disorders
Cough | 10 (17) | 0 (0)
Dyspnea | 10 (17) | 1 (2)
Skin and subcutaneous tissue disorders
Alopecia | 6 (10) | 0 (0)
Dry skin | 6 (10) | 0 (0)
Vascular disorders
Hypertension | 14 (24) | 7 (12)

Clinically relevant adverse reactions include viral tonsilitis (in < 10% of patients) and infusion-related reactions (in 3% of patients).

Table 10: Adverse Reactions Reported in ≥ 10% of ULTOMIRIS-Treated Patients with aHUS in Study ALXN1210-aHUS-312
Body System Adverse Reaction | ALXN1210-aHUS-312 (N=16)
Body System Adverse Reaction | All Grades [Graded per CTCAE v5.0.] (n=16) n (%) | ≥ Grade 3 (n=6) n (%)
Blood and lymphatic system disorders
Anemia | 2 (13) | 1 (6)
Lymphadenopathy | 2 (13) | 0 (0)
Gastrointestinal disorders
Diarrhea | 6 (38) | 0 (0)
Constipation | 4 (25) | 0 (0)
Vomiting | 4 (25) | 1 (6)
Abdominal pain | 3 (19) | 0 (0)
Nausea | 2 (13) | 0 (0)
General disorders and administration site conditions
Pyrexia | 8 (50) | 0 (0)
Infections and infestations
Upper respiratory tract infection [Grouped term includes nasopharyngitis, pharyngitis, upper respiratory tract infection, rhinitis, viral upper respiratory tract infection, rhinovirus infection, viral pharyngitis, rhinorrhea, and oropharyngeal pain.] | 7 (44) | 1 (6)
Gastroenteritis viral | 2 (13) | 2 (13)
Pneumonia | 2 (13) | 1 (6)
Tonsillitis | 2 (13) | 0 (0)
Injury, poisoning and procedural complications
Contusion | 3 (19) | 0 (0)
Investigations
Vitamin D decreased | 3 (19) | 0 (0)
Metabolism and nutrition disorders
Decreased appetite | 2 (13) | 0 (0)
Iron deficiency | 2 (13) | 0 (0)
Musculoskeletal and connective tissue disorders
Myalgia | 3 (19) | 0 (0)
Pain in extremity | 2 (13) | 0 (0)
Nervous system disorders
Headache | 5 (31) | 0 (0)
Respiratory, thoracic and mediastinal disorders
Cough | 3 (19) | 0 (0)
Dyspnea | 2 (13) | 0 (0)
Skin and subcutaneous tissue disorders
Rash | 3 (19) | 0 (0)
Vascular disorders
Hypertension | 4 (25) | 1 (6)
Hypotension | 2 (13) | 0 (0)

Clinically relevant adverse reactions in < 10% of patients include viral infection.

Table 11: Adverse Reactions Reported in ≥ 10% of ULTOMIRIS-Treated Patients from Birth to 16 Years of Age with aHUS in Study ALXN1210-aHUS-312
Body System Adverse Reaction | ALXN1210-aHUS-312
Body System Adverse Reaction | Age 0 to < 2 (N=2) | Age 2 to < 12 (N=12) | Age 12 to 16 (N=1) | Total (N=15)
Body System Adverse Reaction | n (%) | n (%) | n (%) | n (%)
Blood and lymphatic system disorders
Lymphadenopathy | 0 (0) | 2 (17) | 0 (0) | 2 (13)
Gastrointestinal disorders
Diarrhea | 1 (50) | 3 (25) | 1 (100) | 5 (33)
Constipation | 0 (0) | 4 (33) | 0 (0) | 4 (27)
Vomiting | 0 (0) | 3 (25) | 0 (0) | 3 (20)
Abdominal pain | 0 (0) | 2 (17) | 0 (0) | 2 (13)
General disorders and administration site conditions
Pyrexia | 1 (50) | 5 (42) | 1 (100) | 7 (47)
Infections and infestations
Upper respiratory tract infection [Grouped term includes nasopharyngitis, pharyngitis, upper respiratory tract infection, rhinitis, viral upper respiratory tract infection, rhinovirus infection, viral pharyngitis, rhinorrhea, and oropharyngeal pain] | 1 (50) | 6 (50) | 0 (0) | 7 (47)
Gastroenteritis viral | 0 (0) | 2 (17) | 0 (0) | 2 (13)
Tonsillitis | 1 (50) | 1 (8) | 0 (0) | 2 (13)
Injury, poisoning and procedural complications
Contusion | 0 (0) | 2 (17) | 0 (0) | 2 (13)
Investigations
Vitamin D decreased | 0 (0) | 2 (17) | 1 (100) | 3 (20)
Metabolism and nutrition disorders
Decreased appetite | 1 (50) | 1 (8) | 0 (0) | 2 (13)
Iron deficiency | 0 (0) | 2 (17) | 0 (0) | 2 (13)
Musculoskeletal and connective tissue disorders
Myalgia | 1 (50) | 1 (8) | 0 (0) | 2 (13)
Pain in extremity | 0 (0) | 2 (17) | 0 (0) | 2 (13)
Nervous system disorders
Headache | 0 (0) | 4 (33) | 0 (0) | 4 (27)
Respiratory, thoracic and mediastinal disorders
Cough | 0 (0) | 3 (25) | 0 (0) | 3 (20)
Dyspnea | 1 (50) | 1 (8) | 0 (0) | 2 (13)
Skin and subcutaneous tissue disorders
Rash | 1 (50) | 2 (17) | 0 (0) | 3 (20)
Vascular disorders
Hypertension | 1 (50) | 3 (25) | 0 (0) | 4 (27)
Hypotension | 0 (0) | 2 (17) | 0 (0) | 2 (13)

Clinically relevant adverse reactions in < 10% of patients include viral infection.

Generalized Myasthenia Gravis (gMG)

The safety of ULTOMIRIS has been evaluated in 175 adult patients with gMG, including 169 patients who received at least one dose of ULTOMIRIS, 142 patients who were exposed for at least 6 months, and 95 who were exposed for at least 12 months [see Clinical Studies (14.3)]. In a randomized, double-blind, placebo-controlled trial (ALXN1210-MG-306), the most frequent adverse reactions (≥ 10%) with ULTOMIRIS were diarrhea and upper respiratory tract infection. Table 12 describes adverse reactions that occurred at a rate of 5% or more and at greater frequency than placebo. Serious adverse reactions were reported in 20 (23%) patients with gMG receiving ULTOMIRIS and in 14 (16%) patients receiving placebo. The most frequent serious adverse reactions were infections reported in at least 8 (9%) patients treated with ULTOMIRIS and in 4 (4%) patients treated with placebo [see Warnings and Precautions (5.3)]. Of these infections, one fatal case of COVID-19 pneumonia was identified in a patient treated with ULTOMIRIS and one case of infection led to discontinuation of ULTOMIRIS.

Table 12: Adverse Reactions Reported in ≥ 5% and at Greater Frequency than Placebo in ULTOMIRIS-Treated Adult Patients with gMG in Study ALXN1210-MG-306
Body System Adverse Reaction | Number of Patients
Body System Adverse Reaction | ULTOMIRIS (N=86) n (%) | Placebo (N=89) n (%)
Gastrointestinal Disorders
Diarrhea | 13 (15) | 11 (12)
Abdominal pain | 5 (6) | 0
Infections and Infestations
Upper respiratory tract infection | 12 (14) | 7 (8)
Urinary tract infection | 5 (6) | 4 (4)
Musculoskeletal and Connective Tissue Disorders
Back Pain | 7 (8) | 5 (6)
Nervous System Disorders
Dizziness | 8 (9) | 3 (3)

Neuromyelitis Optica Spectrum Disorder (NMOSD)

The safety of ULTOMIRIS has been evaluated in 58 adult patients with NMOSD who received at least one dose of ULTOMIRIS [see Clinical Studies (14.3)]. In Study ALXN1210-NMO-307, an open-label multicenter trial, the most frequent adverse reactions (≥10%) with ULTOMIRIS were COVID-19, headache, back pain, urinary tract infection and arthralgia.

Table 13 describes adverse reactions that occurred at a rate of 5% or more in patients treated with ULTOMIRIS. Serious adverse reactions were reported in 8 (13.8%) patients with NMOSD receiving ULTOMIRIS.

Table 13: Adverse Reactions Reported in ≥ 5% in ULTOMIRIS-Treated Adult Patients with NMOSD in Study ALXN1210-NMO-307
Body System Adverse Reaction | ULTOMIRIS (N=58) n (%)
Blood and Lymphatic System Disorder
Lymphadenopathy | 3 (5)
Gastrointestinal Disorders
Constipation | 4 (7)
Vomiting | 4 (7)
Diarrhea | 3 (5)
Gastroesophageal reflux disease | 3 (5)
General Disorders and Administration Site Reactions
Pyrexia | 5 (9)
Chills | 3 (5)
Fatigue | 3 (5)
Malaise | 3 (5)
Non-cardiac chest pain | 3 (5)
Vaccination site pain | 3 (5)
Infections and Infestations
COVID-19 | 14 (24)
Urinary tract infection | 6 (10)
Cystitis | 5 (9)
Upper respiratory tract infection | 5 (9)
Nasopharyngitis | 3 (5)
Sinusitis | 3 (5)
Injury, Poisoning and Procedural Complications
Infusion related reaction | 4 (7)
Musculoskeletal and Connective Tissue Disorders
Back pain | 7 (12)
Arthralgia | 6 (10)
Myalgia | 3 (5)
Nervous System Disorders
Headache | 14 (24)
Dizziness | 4 (7)
Migraine | 3 (5)
Respiratory, thoracic and mediastinal disorders
Cough | 3 (5)

6.2 Postmarketing Experience

The following adverse reactions have been identified during post-approval use of ULTOMIRIS. Because these reactions are reported voluntarily from a population of uncertain size, it is not always possible to reliably estimate their frequency or establish a causal relationship to ULTOMIRIS exposure.

Adverse Reactions from Postmarketing Spontaneous Reports

- Anaphylaxis [see Warnings and Precautions (5.6)]
- Cases of cholestatic or mixed pattern liver injury with increased serum liver enzymes and bilirubin levels have been reported in adult and pediatric patients with aHUS who were treated with another C5 complement inhibitor. These events occurred within 3 to 27 days after starting treatment. The median time to resolution (or return to baseline) was approximately 3 weeks.

7 DRUG INTERACTIONS

7.1 Plasma Exchange, Plasmapheresis, and Intravenous Immunoglobulins

Concomitant use of ULTOMIRIS with plasma exchange (PE), plasmapheresis (PP), or intravenous immunoglobulin (IVIg) treatment can reduce serum ravulizumab concentrations and requires a supplemental dose of ULTOMIRIS [see Dosage and Administration (2.5)].

7.2 Neonatal Fc Receptor Blockers

Concomitant use of ULTOMIRIS with neonatal Fc receptor (FcRn) blockers (e.g., efgartigimod) may lower systemic exposures and reduce effectiveness of ULTOMIRIS. Closely monitor for reduced effectiveness of ULTOMIRIS.

8 USE IN SPECIFIC POPULATIONS

8.1 Pregnancy

Pregnancy Exposure Registry

There is a pregnancy exposure registry that monitors pregnancy outcomes in women exposed to ULTOMIRIS during pregnancy. Healthcare providers and patients may call 1-833-793-0563 or go to www.UltomirisPregnancyStudy.com to enroll in or to obtain information about the registry.

Risk Summary

There are no available data on ULTOMIRIS use in pregnant women to inform a drug-associated risk of major birth defects, miscarriage, or adverse maternal or fetal outcomes. There are risks to the mother and fetus associated with untreated PNH and aHUS in pregnancy (see Clinical Considerations). Animal studies using a mouse analogue of the ravulizumab-cwvz molecule (murine anti-mouse complement component 5 [C5] antibody) showed increased rates of developmental abnormalities and an increased rate of dead and moribund offspring at doses 0.8-2.2 times the human dose (see Data).

The estimated background risk of major birth defects and miscarriage for the indicated populations is unknown. All pregnancies have a background risk of birth defect, loss, or other adverse outcomes. In the U.S. general population, the estimated background risk of major birth defects and miscarriage in clinically recognized pregnancies is 2-4% and 15-20%, respectively.

Clinical Considerations

Disease-associated Maternal and/or Fetal/neonatal Risk

PNH in pregnancy is associated with adverse maternal outcomes, including worsening cytopenias, thrombotic events, infections, bleeding, miscarriages, and increased maternal mortality, and adverse fetal outcomes, including fetal death and premature delivery.

In pregnancy, aHUS is associated with adverse maternal outcomes, including preeclampsia and preterm delivery, and adverse fetal/neonatal outcomes, including intrauterine growth restriction (IUGR), fetal death and low birth weight.

Data

Animal Data

Animal reproduction studies were conducted in mice using doses of a murine anti-C5 antibody that approximated 1-2.2 times (loading dose) and 0.8-1.8 times (maintenance dose) the recommended human ULTOMIRIS dose, based on a body weight comparison. When animal exposure to the antibody occurred in the time period from before mating until early gestation, no decrease in fertility or reproductive performance was observed. When maternal exposure to the antibody occurred during organogenesis, 2 cases of retinal dysplasia and 1 case of umbilical hernia were observed among 230 offspring born to mothers exposed to the higher antibody dose; however, the exposure did not increase fetal loss or neonatal death. When maternal exposure to the antibody occurred in the time period from implantation through weaning, a higher number of male offspring became moribund or died (1/25 controls, 2/25 low dose group, 5/25 high dose group). Surviving offspring had normal development and reproductive function. Human IgG are known to cross the human placental barrier, and thus ULTOMIRIS may potentially cause terminal complement inhibition in fetal circulation.

8.2 Lactation

Risk summary

There are no data on the presence of ravulizumab-cwvz in human milk, the effect on the breastfed child, or the effect on milk production. Since many medicinal products and immunoglobulins are secreted into human milk, and because of the potential for serious adverse reactions in a nursing child, breastfeeding should be discontinued during treatment and for 8 months after the final dose.

8.4 Pediatric Use

The safety and effectiveness of ULTOMIRIS for the treatment of PNH have been established in pediatric patients aged one month and older. Use of ULTOMIRIS for this indication is supported by evidence from adequate and well-controlled trials in adults with additional pharmacokinetic, efficacy and safety data in pediatric patients aged 9 to 17 years [see Adverse Reactions (6.1), Clinical Pharmacology (12.3), and Clinical Studies (14.1)]. The safety and efficacy for the treatment of pediatric and adult patients with PNH appear similar. Use of ULTOMIRIS in pediatric patients with PNH aged less than 9 years and body weight < 30 kg is based on extrapolation of pharmacokinetic / pharmacodynamic (PK/PD), and efficacy and safety data from aHUS and PNH clinical studies [see Clinical Pharmacology (12.3) and Clinical Studies (14)].

The safety and effectiveness of ULTOMIRIS for the treatment of aHUS have been established in pediatric patients aged one month and older. Use of ULTOMIRIS for this indication is supported by evidence from adequate and well-controlled studies in adults with additional pharmacokinetic, safety, and efficacy data in pediatric patients aged 10 months to < 17 years. The safety and efficacy of ULTOMIRIS for the treatment of aHUS appear similar in pediatric and adult patients [see Adverse Reactions (6.1), and Clinical Studies (14.2)].

The safety and effectiveness of ULTOMIRIS for the treatment of gMG or NMOSD in pediatric patients have not been established.

8.5 Geriatric Use

Clinical studies of ULTOMIRIS did not include sufficient numbers of subjects aged 65 and over (58 patients with PNH, 9 with aHUS, 54 with gMG, and 7 with NMOSD) to determine whether they respond differently from younger subjects.

Other reported clinical experience has not identified differences in responses between elderly and younger patients.

11 DESCRIPTION

Ravulizumab-cwvz, a complement inhibitor, is a humanized monoclonal antibody (mAb) produced in Chinese hamster ovary (CHO) cells. Ravulizumab-cwvz consists of 2 identical 448 amino acid heavy chains and 2 identical 214 amino acid light chains and has a molecular weight of approximately 148 kDa. The constant regions of ravulizumab-cwvz include the human kappa light chain constant region, and the protein engineered "IgG2/4" heavy chain constant region.

The heavy chain CH1 domain, hinge region, and the first 5 amino acids of the CH2 domain match the human IgG2 amino acid sequence, residues 6 to 36 in the CH2 region (common to both human IgG2 and IgG4 amino acid sequences), while the remainder of the CH2 domain and the CH3 domain match the human IgG4 amino acid sequence. The heavy and light chain variable regions that form the human C5 binding site consist of human framework regions grafted to murine complementarity-determining regions.

ULTOMIRIS (ravulizumab-cwvz) injection is a sterile, translucent, clear to yellowish color, preservative-free solution for intravenous use. Each single-dose vial contains 300 mg or 1,100 mg ravulizumab-cwvz at a concentration of 100 mg/mL with a pH of 7.4. Each mL also contains L-arginine (4.33 mg), polysorbate 80 (0.5 mg) (vegetable origin), sodium phosphate dibasic (4.42 mg), sodium phosphate monobasic (4.57 mg), sucrose (50 mg), and Water for Injection, USP.

12 CLINICAL PHARMACOLOGY

12.1 Mechanism of Action

Ravulizumab-cwvz is a terminal complement inhibitor that specifically binds to the complement protein C5 with high affinity, thereby inhibiting its cleavage to C5a (the proinflammatory anaphylatoxin) and C5b (the initiating subunit of the membrane attack complex [MAC or C5b-9]) thus preventing MAC formation. ULTOMIRIS inhibits terminal complement-mediated intravascular hemolysis in patients with PNH and complement-mediated thrombotic microangiopathy (TMA) in patients with aHUS.

The precise mechanism by which ravulizumab-cwvz exerts its therapeutic effect in gMG patients is unknown, but is presumed to involve reduction of terminal complement complex C5b-9 deposition at the neuromuscular junction.

The precise mechanism by which ravulizumab-cwvz exerts its therapeutic effect in NMOSD is unknown, but is presumed to involve inhibition of aquaporin-4 antibody-induced terminal complement C5b-9 deposition.

12.2 Pharmacodynamics

Complete inhibition of serum free C5 (concentration of less than 0.5 mcg/mL) was observed by the end of the first ULTOMIRIS infusion and sustained throughout the entire 26-week treatment period in both adult and pediatric patients with PNH, in the majority (93%) of adult and pediatric patients with aHUS, in all adult patients with gMG, and in the majority (98.3%) of adult patients with NMOSD.

The extent and duration of the pharmacodynamic response in patients with PNH, aHUS, gMG, or NMOSD were exposure-dependent for ULTOMIRIS. Free C5 levels of < 0.5 mcg/mL were correlated with maximal intravascular hemolysis control and complete terminal complement inhibition in patients with PNH.

Complete terminal complement inhibition following initiation of ULTOMIRIS treatment led to normalization of serum LDH by week 4 in complement-inhibitor naïve patients with PNH, and maintained LDH normalization in patients previously treated with eculizumab with PNH [see Clinical Studies (14)].

12.3 Pharmacokinetics

Following ULTOMIRIS treatment, ravulizumab-cwvz pharmacokinetics increase proportionally over a dose range of 200 to 5400 mg. Ravulizumab-cwvz Cmax and Ctrough parameters are presented in Table 14, Table 15, Table 16, and Table 17.

Table 14: Mean (%CV) Pharmacokinetic Parameters Following ULTOMIRIS Treatment in Patients with PNH who are Complement Inhibitor-Naïve and Patients Previously Treated with Eculizumab
 |  | Pediatric Patients |  |  |  | Adult Patients
 |  | ALXN1210-PNH-304 |  |  |  | ALXN1210-PNH-301 |  | ALXN1210-PNH-302
 |  | N | Complement Inhibitor-Naïve | N | Previously Treated with Eculizumab | N | Complement Inhibitor-Naïve | N | Previously Treated with Eculizumab
Cmax (mcg/mL) | LD | 4 | 733 (14.5) | 8 | 885 (19.3) | 125 | 771 (21.5) | 95 | 843 (24.1)
Cmax (mcg/mL) | MD | 4 | 1490 (26.7) | 8 | 1705 (9.7) | 124 | 1,379 (20.0) | 95 | 1,386 (19.4)
Ctrough (mcg/mL) | LD | 4 | 368 (14.7) | 8 | 452 (15.1) | 125 | 391 (35.0) | 96 | 405 (29.9)
Ctrough (mcg/mL) | MD | 4 | 495 (21.3) | 8 | 566 (12.2) | 124 | 473 (33.4) | 95 | 501 (28.6)
Abbreviations: LD = Loading Dose; MD = Maintenance Dose

Table 15: Mean (%CV) Pharmacokinetic Parameters Following ULTOMIRIS Treatment in Patients with aHUS
 |  | Pediatric Patients (ALXN1210-aHUS-312) |  |  |  | Adult Patients (ALXN1210-aHUS-311)
 |  | N | < 20 kg MD Q4W | N | ≥ 20 to < 40 kg MD Q8W | N | ≥ 40 kg MD Q8W
Cmax (mcg/mL) | LD | 8 | 656 (38.1) | 4 | 600 (17.3) | 52 | 754 (35.2)
Cmax (mcg/mL) | MD | 7 | 1,467 (37.8) | 6 | 1,863 (15.3) | 46 | 1,458 (17.6)
Ctrough (mcg/mL) | LD | 9 | 241 (52.1) | 5 | 186 (16.5) | 55 | 313 (33.9)
Ctrough (mcg/mL) | MD | 7 | 683 (46.1) | 6 | 549 (34.1) | 46 | 507 (42.5)
Abbreviations: LD = Loading Dose; MD = Maintenance Dose; Q4W = Every 4 Weeks; Q8W = Every 8 Weeks

Table 16: Mean (%CV) Pharmacokinetic Parameters Following ULTOMIRIS Treatment in Adult Patients with gMG
 |  | N | Adult Patients (ALXN1210-MG-306)
Cmax (mcg/mL) | LD | 86 | 874 (21.1)
Cmax (mcg/mL) | MD | 76 | 1548 (23.2)
Ctrough (mcg/mL) | LD | 85 | 418 (27.6)
Ctrough (mcg/mL) | MD | 70 | 587 (29.6)
Abbreviations: LD = Loading Dose; MD=Maintenance Dose

Table 17: Mean (%CV) Pharmacokinetic Parameters Following ULTOMIRIS Treatment in Adult Patients with NMOSD
 |  | N | Adult Patients (ALXN1210-NMO-307)
Cmax (mcg/mL) | LD | 58 | 935.3 (17.3)
Cmax (mcg/mL) | MD | 56 | 1836.4 (19.4)
Ctrough (mcg/mL) | LD | 58 | 459.1 (19.7)
Ctrough (mcg/mL) | MD | 54 | 796.9 (27.1)
Abbreviations: LD = Loading Dose; MD=Maintenance Dose

Distribution

The mean (standard deviation [SD]) volume of distribution at steady state in patients with PNH, aHUS, gMG, or NMOSD are shown in Table 18.

Elimination

The mean (standard deviation [SD]) terminal elimination half-life and clearance of ravulizumab-cwvz are shown in Table 18.

Table 18: Distribution, Biotransformation, and Elimination Parameters Following ULTOMIRIS Treatment
 | Adult and Pediatric Patients with PNH | Adult and Pediatric Patients with aHUS | Adult Patients with gMG | Adult Patients with NMOSD
Distribution
Volume of distribution at steady state (liters) Mean (SD) | 5.30 (0.95) | 5.22 (1.85) | 5.74 (1.16) | 4.77 (0.819)
Biotransformation and Elimination
Terminal elimination half-life (days) Mean (SD) | 49.6 (9.08) | 51.8 (16.2) | 56.6 (8.36) | 64.3 (11.0)
Clearance (liters/day) Mean (SD) | 0.08 (0.02) | 0.08 (0.04) | 0.08 (0.02) | 0.05 (0.016)

Specific Populations

No clinically significant differences in the pharmacokinetics of ravulizumab-cwvz were observed based on sex, age (10 months to 83 years), race, hepatic impairment, or any degree of renal impairment, including patients with proteinuria or receiving dialysis.

Body weight was a clinically significant covariate on the pharmacokinetics of ravulizumab-cwvz.

Drug Interactions

No drug-drug interaction studies have been performed.

Neonatal Fc Receptor blocker treatment may interfere with the endosomal neonatal FcRn recycling mechanism of monoclonal antibodies such as ravulizumab and thereby decrease serum ravulizumab concentrations [see Drug Interactions (7.1, 7.2)].

Concomitant PE, PP, or IVIg treatment requires a supplemental dose of ULTOMIRIS [see Dosage and Administration (2.5)].

12.6 Immunogenicity

The observed incidence of anti-drug antibodies is highly dependent on the sensitivity and specificity of the assay. Differences in assay methods preclude meaningful comparisons of the incidence of anti-drug antibodies in the studies described below with the incidence of anti-drug antibodies in other studies, including those of ULTOMIRIS or other ravulizumab-cwvz products.

The immunogenicity of ravulizumab-cwvz has been evaluated using an enzyme-linked immunosorbent assay (ELISA) for the detection of binding anti-ravulizumab-cwvz antibodies. For patients whose sera tested positive in the screening immunoassay, an in vitro biological assay was performed to detect neutralizing antibodies.

In clinical studies with ULTOMIRIS, treatment-emergent antibodies to ravulizumab-cwvz were detected in 1 of 219 (0.5%) patients with PNH [see Clinical Studies (14.1)] and 1 of 71 (1.4%) patients with aHUS [see Clinical Studies (14.2)]. In these 2 patient populations, the observed ADA were non-neutralizing with no apparent impact on PK, safety, or efficacy. In the gMG study (N=86) and NMOSD study (N=58), no treatment-emergent antibodies to ravulizumab-cwvz were detected [see Clinical Studies (14.3 & 14.4)].

However, the assay used to measure anti-drug antibodies (ADA) is subject to interference by serum ravulizumab-cwvz, possibly resulting in an underestimation of the incidence of antibody formation. Due to the limitation of the assay conditions, the potential clinical impact of antibodies to ravulizumab-cwvz is not known.

13 NONCLINICAL TOXICOLOGY

13.1 Carcinogenesis, Mutagenesis, Impairment of Fertility

Long-term animal carcinogenicity studies of ravulizumab-cwvz have not been conducted.

Genotoxicity studies have not been conducted with ravulizumab-cwvz.

Effects of ravulizumab-cwvz upon fertility have not been studied in animals. Intravenous injections of male and female mice with a murine anti-C5 antibody at up to 0.8-2.2 times the equivalent of the clinical dose of ULTOMIRIS had no adverse effects on mating or fertility.

14 CLINICAL STUDIES

14.1 Paroxysmal Nocturnal Hemoglobinuria (PNH)

The safety and efficacy of ULTOMIRIS in adult patients with PNH was assessed in 2 open-label, randomized, active-controlled, non-inferiority Phase 3 studies: PNH Study 301 and PNH Study 302. Study 301 enrolled patients with PNH who were complement inhibitor-naïve and had active hemolysis. Study 302 enrolled patients with PNH who were clinically stable after having been treated with eculizumab for at least the past 6 months. The safety and efficacy of ULTOMIRIS in pediatric patients with PNH was assessed in PNH Study 304, an open-label, Phase 3 study conducted in eculizumab-experienced and complement inhibitor treatment-naïve pediatric patients with PNH.

In Study 301 and Study 302, adults with PNH were dosed with ULTOMIRIS administered intravenously in accordance with the weight-based dosing described in Section 2.3 (4 infusions of ULTOMIRIS over 26 weeks) above. Eculizumab was administered on Days 1, 8, 15, and 22, followed by maintenance treatment with 900 mg of eculizumab on Day 29 and every 2 weeks (q2w) thereafter for a total of 26 weeks of treatment, according to the approved dosing regimen of eculizumab which was the standard-of-care for PNH at the time of the studies.

Patients were vaccinated against meningococcal infection prior to or at the time of initiating treatment with ULTOMIRIS or eculizumab, or received prophylactic treatment with appropriate antibiotics until 2 weeks after vaccination. Prophylactic treatment with appropriate antibiotics beyond 2 weeks after vaccination was at the discretion of the provider.

Study in Complement-Inhibitor Naïve Adult Patients with PNH

The Complement-Inhibitor Naïve Study [ALXN1210-PNH-301; NCT02946463] was a 26-week, multicenter, open-label, randomized, active-controlled, non-inferiority Phase 3 study conducted in 246 patients naïve to complement inhibitor treatment prior to study entry.

Patients with PNH with flow cytometric confirmation of at least 5% PNH cells were randomized 1:1 to either intravenously administered ULTOMIRIS or eculizumab. The mean total PNH granulocyte clone size was 85%, the mean total PNH monocyte clone size was 88%, and the mean total PNH RBC clone size was 39%. Ninety-eight percent of patients had a documented PNH-associated condition diagnosed prior to enrollment on the trial: anemia (85%), hemoglobinuria (63%), history of aplastic anemia (32%), history of renal failure (12%), myelodysplastic syndrome (5%), pregnancy complications (3%), and other (16%). Major baseline characteristics were balanced between treatment groups. Table 19 provides the baseline characteristics for the patients enrolled in the complement-inhibitor naïve study.

Table 19: Baseline Characteristics in the Complement-Inhibitor Naïve Study
Parameter | Statistics | ULTOMIRIS (N=125) | Eculizumab (N=121)
Age (years) at first infusion in study | Mean (SD) Min, max | 44.8 (15.2) 18, 83 | 46.2 (16.2) 18, 86
Sex
Male | n (%) | 65 (52.0) | 69 (57.0)
Race
Asian | n (%) | 72 (57.6) | 57 (47.1)
White | n (%) | 43 (34.4) | 51 (42.1)
Black or African American | n (%) | 2 (1.6) | 4 (3.3)
American Indian or Alaska Native | n (%) | 1 (0.8) | 1 (0.8)
Other | n (%) | 4 (3.2) | 4 (3.3)
Not reported | n (%) | 3 (2.4) | 4 (3.3)
Pre-treatment LDH levels (U/L) | Median Min, max | 1513.5 (378.0, 3759.5) | 1445.0 (423.5, 3139.5)
Units of pRBC/whole blood transfused within 12 months prior to first dose | Median Min, max | 6.0 (1, 44) | 6.0 (1, 32)
Antithrombotic agents used within 28 days prior to first dose | n (%) | 22 (17.6) | 22 (18.2)
Patients with a history of MAVE | n (%) | 17 (13.6) | 25 (20.7)
Patients with a history of thrombosis | n (%) | 17 (13.6) | 20 (16.5)
Patients with concomitant anticoagulant treatment | n (%) | 23 (18.4) | 28 (23.1)
Abbreviations: LDH = lactate dehydrogenase; max = maximum; min = minimum; MAVE = major adverse vascular event; pRBC = packed red blood cell; SD = standard deviation

Efficacy was established based upon transfusion avoidance and hemolysis as directly measured by normalization of LDH levels. Transfusion avoidance was defined as patients who did not receive a transfusion and did not meet the protocol specified guidelines for transfusion from baseline up to Day 183. Supportive efficacy data included the percent change from baseline in LDH levels, the proportion of patients with breakthrough hemolysis defined as at least one new or worsening symptom or sign of intravascular hemolysis in the presence of elevated LDH ≥ 2 × ULN, after prior LDH reduction to < 1.5 × ULN on therapy and the proportion of patients with stabilized hemoglobin.

Non-inferiority of ULTOMIRIS to eculizumab was demonstrated across endpoints in the complement-inhibitor naïve treatment population described in Table 20 below.

Table 20: Efficacy Results in the Complement-Inhibitor Naïve Study
 | ULTOMIRIS (N=125) | Eculizumab (N=121) | Statistic for Comparison | Treatment Effect (95% CI)
Transfusion avoidance rate | 73.6% | 66.1% | Difference in rate | 6.8 (-4.66, 18.14)
LDH normalization | 53.6% | 49.4% | Odds ratio | 1.19 (0.80, 1.77)
LDH percent change | -76.84% | -76.02% | Difference in % change from baseline | -0.83 (-5.21, 3.56)
Breakthrough hemolysis | 4.0% | 10.7% | Difference in rate | -6.7 (-14.21, 0.18)
Hemoglobin stabilization | 68.0% | 64.5% | Difference in rate | 2.9 (-8.80, 14.64)
For the transfusion avoidance endpoint, treatment differences (95% CIs) are based on estimated differences in percent with 95% CI. For the lactate dehydrogenase normalization endpoint, the adjusted prevalence within each treatment is displayed.
Abbreviations: LDH = lactate dehydrogenase; CI = confidence interval

There was no observable difference in fatigue between ULTOMIRIS and eculizumab after 26 weeks of treatment compared to baseline as measured by the FACIT-fatigue instrument. Patient-reported fatigue may be an under- or over-estimation because patients were not blinded to treatment assignment.

Study in Eculizumab-Experienced Adult Patients with PNH

The study in eculizumab-experienced patients [ALXN1210-PNH-302; NCT03056040] was a 26-week, multicenter, open-label, randomized, active-controlled, non-inferiority Phase 3 study conducted in 195 patients with PNH who were clinically stable after having been treated with eculizumab for at least the past 6 months.

Patients who demonstrated clinically stable disease after being treated with eculizumab for at least the prior 6 months were randomized 1:1 to either continue eculizumab or to switch to ULTOMIRIS administered intravenously. The mean total PNH granulocyte clone size was 83%, the mean total PNH monocyte clone size was 86%, and the mean total PNH RBC clone size was 60%. Ninety-five percent of patients had a documented PNH-associated condition diagnosed prior to enrollment in the trial: anemia (67%), hematuria or hemoglobinuria (49%), history of aplastic anemia (37%), history of renal failure (9%), myelodysplastic syndrome (5%), pregnancy complication (7%), and other (14%). Major baseline characteristics were balanced between the 2 treatment groups. Table 21 provides the baseline characteristics for the patients enrolled in the eculizumab-experienced study.

Table 21: Baseline Characteristics in Eculizumab-Experienced Adult Patients with PNH
Parameter | Statistics | ULTOMIRIS (N=97) | Eculizumab (N=98)
Age (years) at first infusion in study | Mean (SD) Min, max | 46.6 (14.41) 18, 79 | 48.8 (13.97) 23, 77
Race | n (%)
White | n (%) | 50 (51.5) | 61 (62.2)
Asian | n (%) | 23 (23.7) | 19 (19.4)
Black or African American | n (%) | 5 (5.2) | 3 (3.1)
Other | n (%) | 2 (2.1) | 1 (1.0)
Not reported | n (%) | 13 (13.4) | 13 (13.3)
Unknown | n (%) | 3 (3.1) | 1 (1.0)
Multiple | n (%) | 1 (1.0) | 0
Sex | n (%)
Male | n (%) | 50 (51.5) | 48 (49.0)
Pre-treatment LDH levels (U/L) | Median Min, max | 224.0 135.0, 383.5 | 234.0 100.0, 365.5
Units of pRBC/whole blood transfused within 12 months prior to first dose | Median Min, max | 4.0 (1, 32) | 2.5 (2, 15)
Antithrombotic agents used within 28 days prior to first dose | n (%) | 20 (20.6) | 13 (13.3)
Patients with a history of MAVE | n (%) | 28 (28.9) | 22 (22.4)
Patients with a history of thrombosis | n (%) | 27 (27.8) | 21 (21.4)
Patients with concomitant anticoagulant treatment | n (%) | 22 (22.7) | 16 (16.3)
Abbreviations: LDH = lactate dehydrogenase; max = maximum; min = minimum; MAVE = major adverse vascular event; pRBC = packed red blood cell; SD = standard deviation

Efficacy was established based on hemolysis as measured by LDH percent change from baseline to Day 183 and supportive efficacy data was transfusion avoidance, proportion of patients with stabilized hemoglobin, and the proportion of patients with breakthrough hemolysis through Day 183.

Non-inferiority of ULTOMIRIS to eculizumab was demonstrated across endpoints in the patients with PNH previously treated with eculizumab described in Table 22 below.

Table 22: Efficacy Results in the Eculizumab-Experienced Adult Patients with PNH Eculizumab-Experienced Study
 | ULTOMIRIS N = 97 | Eculizumab N = 98 | Statistic for Comparison | Treatment Effect (95% CI)
LDH percent change | -0.82% | 8.4% | Difference in % change from baseline | 9.2 (-0.42, 18.8)
Breakthrough hemolysis | 0% | 5.1% | Difference in rate | 5.1 (-8.9, 19.0)
Transfusion avoidance | 87.6 % | 82.7% | Difference in rate | 5.5 (-4.3, 15.7)
Hemoglobin stabilization | 76.3% | 75.5% | Difference in rate | 1.4 (-10.4, 13.3)
Abbreviations: CI = confidence interval; LDH = lactate dehydrogenase

There was no observable difference in fatigue between ULTOMIRIS and eculizumab after 26 weeks of treatment compared to baseline as measured by the FACIT-fatigue instrument. Patient-reported fatigue may be an under-or over-estimation because patients were not blinded to treatment assignment.

Study in Eculizumab-Experienced and Complement-Inhibitor Naïve Pediatric Patients with PNH

The pediatric study, ALXN1210-PNH-304 (NCT03406507), was a multi-center, open-label Phase 3 study conducted in eculizumab-experienced and complement inhibitor treatment-naïve pediatric patients with PNH. A total of 13 pediatric patients with PNH completed intravenously administered ULTOMIRIS treatment during the Primary Evaluation Period (26 weeks). Five of the 13 patients had never been treated with complement inhibitors and 8 patients were treated with eculizumab. Eleven of the thirteen patients were between 12 and 17 years of age at first infusion, with 2 patients under 12 years old (11 and 9 years old). Table 23 presents the baseline characteristics of the pediatric patients enrolled in Study ALXN1210-PNH-304.

Table 23: Baseline Characteristics for Pediatric Patients with PNH
Variable | Complement Inhibitor Treatment-naïve Patients (N = 5) | Eculizumab-Experienced Patients (N = 8) | All Patients (N = 13)
Sex, n (%)
Male | 4 (80.0) | 1 (12.5) | 5 (38.5)
Female | 1 (20.0) | 7 (87.5) | 8 (61.5)
Age at first infusion (years)
Mean (SD) | 14.4 (2.2) | 14.4 (3.1) | 14.4 (2.7)
Median (min, max) | 15.0 (11, 17) | 15.0 (9, 17) | 15.0 (9, 17)
Age at first infusion (years) category, n (%)
< 12 years | 1 (20.0) | 1 (12.5) | 2 (15.4)
≥ 12 years | 4 (80.0) | 7 (87.5) | 11 (84.6)
Baseline weight (kg)
Mean (SD) | 56.3 (11.6) | 56.3 (12.2) | 56.3 (11.5)
Median (min, max) | 55.6 (39.5, 72.0) | 55.5 (36.7, 69.0) | 55.6 (36.7, 72.0)
Baseline weight (kg) category, n (%)
≥ 30 to < 40 kg | 1 (20.0) | 1 (12.5) | 2 (15.4)
≥ 40 to < 60 kg | 3 (60.0) | 4 (50.0) | 7 (53.8)
≥ 60 to < 100 kg | 1 (20.0) | 3 (37.5) | 4 (30.8)
Units of pRBC/whole blood transfused within 12 months prior to first dose
Median (min, max) | 7.0 (3, 11) | 2.0 (2, 2) | -
Pre-treatment LDH levels (U/L)
Median (min, max) | 588.5 (444, 2269.7) | 251.5 (140.5, 487) | -
Note: Percentages were based on the total number of patients in each cohort, or overall.
Abbreviations: LDH = lactate dehydrogenase; kg = kilogram; max = maximum; min = minimum; pRBC = packed red blood cells; SD = standard deviation

Based on body weight, patients received a loading dose of ULTOMIRIS on Day 1, followed by maintenance treatment on Day 15 and once every 8 weeks (q8w) thereafter for patients weighing ≥ 20 kg, or once every 4 weeks (q4w) for patients weighing < 20 kg. For patients who entered the study on eculizumab therapy, Day 1 of study treatment was planned to occur 2 weeks from the patient's last dose of eculizumab.

The weight-based dose regimen of ravulizumab-cwvz provided inhibition of terminal complement in all patients throughout the entire 26-week treatment period regardless of prior experience with eculizumab. Following initiation of ravulizumab-cwvz treatment, steady-state therapeutic serum concentrations of ravulizumab-cwvz were achieved after the first dose and maintained throughout the primary evaluation period in both cohorts. Three of 5 complement inhibitor treatment-naïve patients and 6 out of 8 eculizumab-experienced patients achieved hemoglobin stabilization by Week 26, respectively. Transfusion avoidance was reached for 11 out of 13 of patients during the 26-week Primary Evaluation Period. One patient experienced breakthrough hemolysis during the extension period. Table 24 presents secondary efficacy outcomes for the primary evaluation period.

Table 24: Efficacy Outcomes from the 26-Week Primary Evaluation Period of Pediatric Patient Study in PNH (ALXN1210-PNH-304)
Endpoint | Treatment Naïve (N = 5) | Eculizumab Experienced (N = 8)
LDH percent change from baseline (%) [95% CIs for the mean obtained from t-distribution were presented.] | -47.9 (-113.4, 17.5) | 4.7 (-36.7, 46.0)
Transfusion avoidance (%) [95% CIs for the proportion were based on exact confidence limits using the Clopper-Pearson method.] | 60.0 (14.7, 94.7) | 100.0 (63.1, 100.0)
Change in FACIT-Fatigue | 3.4 (-4.2, 11.0) | 1.3 (-3.1, 5.7)
Hemoglobin stabilization (%) | 60.0 (14.7, 94.7) | 75.0 (34.9, 96.8)
Breakthrough hemolysis (%) | 0 | 0 [No patients experienced breakthrough hemolysis during the primary evaluation period. One patient experienced breakthrough hemolysis at 1.8 years during the extension period; however, at the time of the breakthrough hemolysis event the patient had adequate C5 inhibition (free C5 < 0.5 mcg/mL).]
Abbreviations: FACIT = Functional Assessment of Chronic Illness Therapy; LDH = lactate dehydrogenase

A clinically relevant improvement from baseline in fatigue as assessed by Pediatric FACIT-Fatigue (i.e., mean improvement of > 3 units for Pediatric FACIT Fatigue scores) was sustained throughout the primary evaluation period in the 5-complement inhibitor treatment-naïve patients. A slight improvement was also observed in eculizumab-experienced patients. However, patient-reported fatigue may be an under- or over-estimation because patients were not blinded to treatment assignment.

The efficacy of ULTOMIRIS in pediatric patients with PNH is similar to that observed in adult patients with PNH enrolled in pivotal studies.

14.2 Atypical Hemolytic Uremic Syndrome (aHUS)

The efficacy of ULTOMIRIS administered intravenously in patients with aHUS was assessed in 2 open-label, single-arm studies. Study ALXN1210-aHUS-311 enrolled adult patients who displayed signs of TMA. In order to qualify for enrollment, patients were required to have a platelet count ≤ 150 × 10^9/L, evidence of hemolysis such as an elevation in serum LDH, and serum creatinine above the upper limits of normal or required dialysis.

Study ALXN1210-aHUS-312 enrolled pediatric patients who displayed signs of TMA. In order to qualify for enrollment, patients were required to have a platelet count ≤ 150 × 10^9/L, evidence of hemolysis such as an elevation in serum LDH, and serum creatinine level ≥ 97.5% percentile at screening or required dialysis. In both studies, enrollment criteria excluded patients presenting with TMA due to a disintegrin and metalloproteinase with a thrombospondin type 1 motif, member 13 (ADAMTS13) deficiency, Shiga toxin Escherichia coli related hemolytic uremic syndrome (STEC-HUS) and genetic defect in cobalamin C metabolism. Patients with confirmed diagnosis of STEC-HUS after enrollment were excluded from the efficacy evaluation.

Study in Adult Patients with aHUS

The adult study [ALXN1210-aHUS-311; NCT02949128] was conducted in patients who were naïve to complement inhibitor treatment prior to study entry. The study consisted of a 26-week Initial Evaluation Period and patients were allowed to enter an extension period for up to 4.5 years. All patients received ULTOMIRIS administered intravenously according to their weight [see Dosage and Administration (2.3)].

A total of 56 patients with aHUS were evaluated for efficacy. Ninety-three percent of patients had extra-renal signs (cardiovascular, pulmonary, central nervous system, gastrointestinal, skin, skeletal muscle) or symptoms of aHUS at baseline. At baseline, 71.4% (n = 40) of patients had Stage 5 chronic kidney disease (CKD). Fourteen percent had a medical history of kidney transplant and 51.8% were on dialysis at study entry. Eight patients entered the study with evidence of TMA for > 3 days after childbirth (i.e., postpartum).

Table 25 presents the demographics and baseline characteristics of the 56 adult patients enrolled in Study ALXN1210-aHUS-311 that constituted the Full Analysis Set.

Table 25: Demographics and Baseline Characteristics in Study ALXN1210-aHUS-311
Parameter | Statistics | ULTOMIRIS (N=56)
Age at time of first infusion (years) | Mean (SD) Min, max | 42.2 (14.98) 19.5, 76.6
Sex
Female | n (%) | 37 (66.1)
Race [Patients can have multiple races selected.] | n (%)
White |  | 29 (51.8)
Asian |  | 15 (26.8)
Unknown |  | 8 (14.3)
Other |  | 4 (7.1)
Platelets (10^9/L) blood [normal range 130 to 400 × 10^9/L] | n Median (min,max) | 56 95.25 (18, 473)
Hemoglobin (g/L) blood [normal range 115 to 160 g/L (female), 130 to 175 g/L (male)] | n Median (min,max) | 56 85.00 (60.5, 140)
LDH (U/L) serum [normal range 120 to 246 U/L] | n Median (min,max) | 56 508.00 (229.5, 3249)
eGFR (mL/min/1.73 m^2) [normal range ≥ 60 mL/min/1.73 m^2] | n (%) Mean (SD) Median (min,max) | 55 15.86 (14.815) 10.00 (4, 80)
Note: Percentages are based on the total number of patients.
Abbreviations: eGFR = estimated glomerular filtration rate; LDH = lactate dehydrogenase; max = maximum; min = minimum; SD = standard deviation

The efficacy evaluation was based on Complete TMA Response during the 26-week Initial Evaluation Period, as evidenced by normalization of hematological parameters (platelet count and LDH) and ≥ 25% improvement in serum creatinine from baseline. Patients had to meet each Complete TMA Response criteria at 2 separate assessments obtained at least 4 weeks (28 days) apart, and any measurement in between.

Complete TMA Response was observed in 30 of the 56 patients (54%) during the 26-week Initial Evaluation Period as shown in Table 26.

Table 26: Efficacy Results in aHUS during the 26-Week Initial Evaluation Period (ALXN1210-aHUS-311)
 | Total | Responder
 | Total | n | Proportion (95% CI) [95% CIs for the proportion were based on exact confidence limits using the Clopper-Pearson method.]
Complete TMA Response | 56 | 30 | 0.54 (0.40, 0.67)
Components of Complete TMA Response
Platelet count normalization | 56 | 47 | 0.84 (0.72, 0.92)
LDH normalization | 56 | 43 | 0.77 (0.64, 0.87)
≥ 25% improvement in serum creatinine from baseline | 56 | 33 | 0.59 (0.45, 0.72)
Hematologic normalization | 56 | 41 | 0.73 (0.60, 0.84)
Abbreviations: CI = confidence interval; LDH = lactate dehydrogenase; TMA = thrombotic microangiopathy

One additional patient had a Complete TMA Response that was confirmed after the 26-week Initial Evaluation Period. Complete TMA Response was achieved at a median time of 86 days (range: 7 to 169 days). The median duration of Complete TMA Response was 7.97 months (range: 2.52 to 16.69 months). All responses were maintained through all available follow-up.

Other endpoints included platelet count change from baseline, dialysis requirement, and renal function as evaluated by estimated glomerular filtration rate (eGFR).

An increase in mean platelet count was observed after commencement of ULTOMIRIS treatment, increasing from 118.52 × 10^9/L at baseline to 240.34 ×10^9/L at Day 8 and remaining above 227 × 10^9/L at all subsequent visits in the Initial Evaluation Period (26 weeks).

Renal function, as measured by eGFR, was improved or maintained during ULTOMIRIS therapy. The mean eGFR (+/- SD) increased from 15.86 (14.82) at baseline to 51.83 (39.16) by 26 weeks. In patients with Complete TMA Response, renal function continued to improve after the Complete TMA Response was achieved.

Seventeen of the 29 patients (59%) who required dialysis at study entry discontinued dialysis by the end of the available follow-up and 6 of 27 (22%) patients were off dialysis at baseline were on dialysis at last available follow-up.

Study in Pediatric Patients with aHUS

The Pediatric Study [ALXN1210-aHUS-312; NCT03131219] is a 26-week ongoing, multicenter, single-arm study conducted in 16 pediatric patients. All patients received ULTOMIRIS administered intravenously according to their weight [see Dosage and Administration (2.3)].

A total of 14 eculizumab-naïve patients with documented diagnosis of aHUS were enrolled and included in this interim analysis. The median age at the time of first infusion was 5.2 years (range 0.9, 17.3 years). The overall mean weight at Baseline was 19.8 kg; half of the patients were in the baseline weight category ≥ 10 to < 20 kg. The majority of patients (71%) had pretreatment extra-renal signs (cardiovascular, pulmonary, central nervous system, gastrointestinal, skin, skeletal muscle) or symptoms of aHUS at baseline. At baseline, 35.7% (n = 5) of patients had a CKD Stage 5. Seven percent had history of prior kidney transplant and 35.7% were on dialysis at study entry.

Table 27 presents the baseline characteristics of the pediatric patients enrolled in Study ALXN1210-aHUS-312.

Table 27: Demographics and Baseline Characteristics in Study ALXN1210-aHUS-312
Parameter | Statistics | ULTOMIRIS (N = 14)
Age at time of first infusion (years) category | n (%)
Birth to < 2 years |  | 2 (14.3)
2 to < 6 years |  | 7 (50.0)
6 to < 12 years |  | 4 (28.6)
12 to < 18 years |  | 1 (7.1)
Sex | n (%)
Female |  | 9 (64.3)
Race [Patients can have multiple races selected.] | n (%)
White |  | 7 (50.0)
Asian |  | 4 (28.6)
Black or African American |  | 2 (14.3)
American Indian or Alaskan Native |  | 1 (7.1)
Unknown |  | 1 (7.1)
Platelets (10^9/L) blood [normal range 229 to 533 × 10^9/L] | Median (min, max) | 64.00 (14, 125)
Hemoglobin (g/L) blood [normal range 107 to 131 g/L] | Median (min, max) | 74.25 (32, 106)
LDH (U/L) serum [normal range 165 to 395 U/L] | Median (min, max) | 2077.00 (772, 4985)
eGFR (mL/min/1.73 m^2) [normal range ≥ 60 mL/min/1.73 m^2] | Mean (SD) Median (min, max) | 28.4 (23.11) 22.0 (10, 84)
Note: Percentages are based on the total number of patients.
Abbreviations: eGFR = estimated glomerular filtration rate; LDH = lactate dehydrogenase; max = maximum; min = minimum

Efficacy evaluation was based upon Complete TMA Response during the 26-week Initial Evaluation Period, as evidenced by normalization of hematological parameters (platelet count and LDH) and ≥ 25% improvement in serum creatinine from baseline. Patients had to meet all Complete TMA Response criteria at 2 separate assessments obtained at least 4 weeks (28 days) apart, and any measurement in between.

Complete TMA Response was observed in 10 of the 14 patients (71%) during the 26-week Initial Evaluation Period as shown in Table 28.

Table 28: Efficacy Results in aHUS during the 26-Week Initial Evaluation Period (ALXN1210-aHUS-312)
 | Total | Responder
 | Total | n | Proportion (95% CI) [95% CIs for the proportion were based on exact confidence limits using the Clopper-Pearson method.]
Complete TMA Response | 14 | 10 | 0.71 (0.42, 0.92)
Components of Complete TMA Response
Platelet count normalization | 14 | 13 | 0.93 (0.66, 0.99)
LDH normalization | 14 | 12 | 0.86 (0.57, 0.98)
≥ 25% improvement in serum creatinine from baseline | 14 | 11 | 0.79 (0.49, 0.95)
Hematologic normalization | 14 | 12 | 0.86 (0.57, 0.98)
Note: One patient withdrew from study after receiving 2 doses of ravulizumab-cwvz.
Abbreviations: CI = confidence interval; LDH = lactate dehydrogenase; TMA = thrombotic microangiopathy

Complete TMA Response during the Initial Evaluation Period was achieved at a median time of 30 days (range:15 to 88 days). The median duration of Complete TMA Response was 5.08 months (range: 3.08 to 5.54 months). All responses were maintained through all available follow-up.

Other endpoints included platelet count change from baseline, dialysis requirement, and renal function as evaluated by eGFR.

An increase in mean platelet count was observed after commencement of ULTOMIRIS treatment, increasing from 60.50 × 10^9/L at baseline to 296.67 × 10^9/L at Day 8 and remained above 296 × 10^9/L at all subsequent visits in the Initial Evaluation Period (26 weeks). The mean eGFR (+/- SD) increased from 28.4 (23.11) at baseline to 108.0 (63.21) by 26 weeks.

Four of the 5 patients who required dialysis at study entry were able to discontinue dialysis after the first month in study and for the duration of ULTOMIRIS treatment. No patient started dialysis during the study.

14.3 Generalized Myasthenia Gravis (gMG)

The efficacy of ULTOMIRIS for the treatment of gMG was demonstrated in a randomized, double-blind, placebo-controlled, multicenter study (ALXN1210-MG-306; NCT03920293). Patients were randomized 1:1 to either receive ULTOMIRIS (n=86) or placebo (n=89) for 26 weeks. ULTOMIRIS was administered intravenously according to the weight-based recommended dosage [see Dosage and Administration (2.3)].

Patients with gMG with a positive serologic test for anti-AChR antibodies, Myasthenia Gravis Foundation of America (MGFA) clinical classification class II to IV, and Myasthenia Gravis-Activities of Daily Living (MG-ADL) total score ≥ 6 were enrolled. Baseline and disease characteristics were similar between treatment groups (including age at first dose [mean of 58 years for ULTOMIRIS versus 53 years for placebo], gender [51% female for ULTOMIRIS versus 51% female for placebo], race as White, Asian, and Black or African American [78%, 17%, and 2% for ULTOMIRIS versus 69%, 18%, and 5% for placebo, respectively], and duration of MG since diagnosis [mean of 10 years, ranging from 0.5 to 39.5 years, for ULTOMIRIS versus mean of 10.0 years, ranging from 0.5 to 36.1 years, for placebo].

Over 80% of patients were receiving acetylcholinesterase inhibitors, 70% were receiving corticosteroids, and 68% were receiving non-steroidal immunosuppressants (ISTs) at study entry. Patients on concomitant medications to treat gMG were permitted to continue on therapy throughout the course of the study.

The primary efficacy endpoint was a comparison of the change from baseline between treatment groups in the MG-ADL total score at Week 26. The MG-ADL is a categorical scale that assesses the impact on daily function of 8 signs or symptoms that are typically affected in gMG. Each item is assessed on a 4-point scale where a score of 0 represents normal function and a score of 3 represents loss of ability to perform that function. The total score ranges from 0 to 24, with the higher scores indicating more impairment.

The secondary endpoints, also assessed from baseline to Week 26, included the change in the Quantitative MG total score (QMG). The QMG is a 13-item categorical scale assessing muscle weakness. Each item is assessed on a 4-point scale where a score of 0 represents no weakness and a score of 3 represents severe weakness. A total score ranges from 0 to 39, where higher scores indicate more severe impairment.

Other secondary endpoints included the proportion of patients with improvements of at least 5 and 3 points in the QMG and MG-ADL total scores, respectively.

Treatment with ULTOMIRIS demonstrated a statistically significant change in the MG-ADL and QMG total scores from baseline at Week 26 as compared to placebo (Table 29).

Table 29: Efficacy Results in Patients with gMG
Efficacy Endpoints: Change from Baseline at Week 26 | Placebo (n = 89) LS Mean | ULTOMIRIS (n = 86) LS Mean | Treatment Effect (95% CI) | p-value [p-value calculated using mixed effect model for repeated measures]
Primary Endpoint
MG-ADL | -1.4 | -3.1 | -1.6 (-2.6, -0.7) | < 0.001
Secondary Endpoint
QMG | -0.8 | -2.8 | -2.0 (-3.2, -0.8) | < 0.001
Abbreviations: CI = confidence interval, LS = least squares; MG-ADL = Myasthenia Gravis Activities of Daily Living profile; QMG = Quantitative Myasthenia Gravis score for disease severity

The proportion of QMG responders with at least a 5-point improvement at week 26 was greater for ULTOMIRIS (30.0%) compared to placebo (11.3%) p = 0.005. The proportion of MG-ADL responders with at least a 3-point improvement at week 26 was also greater for ULTOMIRIS (56.7%) compared to placebo (34.1%). The proportion of clinical responders at higher response thresholds (≥ 4-, 5-, 6-, 7-, or 8-point improvement on MG-ADL, and ≥ 6-, 7-, 8-, 9-, or 10-point improvement on QMG) was consistently greater for ULTOMIRIS compared to placebo.

Figure 1: Change from Baseline in MG-ADL Total Score (A) and QMG Total Score (B) Through Week 26 of the Randomized Controlled Period of ALXN1210-MG-306 (Mean and 95% CI)

Note: *p<0.001 versus placebo

14.4 Neuromyelitis Optica Spectrum Disorder (NMOSD)

The efficacy and safety of ULTOMIRIS in adult patients with anti-AQP4 antibody positive NMOSD was assessed in an open-label multicenter study, Study ALXN1210-NMO-307 (NCT04291262). Patients participating in Study ALXN1210-NMO-307 received ULTOMIRIS intravenously in the Primary Treatment Period that ended when the last enrolled patient completed (or discontinued prior to) 50 weeks on study, representing a median study duration of 73.5 weeks (minimum 13.7, maximum 117.7). Efficacy assessments were based on a comparison of patients in Study ALXN1210-NMO-307 with an external placebo control group from another study (Study ECU-NMO-301, NCT01892345) composed of a comparable population of adult patients with anti-AQP4 antibody positive NMOSD.

Study ALXN1210-NMO-307 enrolled 58 adult patients with NMOSD who had a positive serologic test for anti-AQP4 antibodies, at least 1 relapse in the last 12 months prior to the Screening Period, and an Expanded Disability Status Scale (EDSS) score ≤ 7. In the external placebo control group, eligibility criteria were similar except patients were required to have at least 2 relapses in last 12 months or 3 relapses in the last 24 months with at least 1 relapse in the 12 months prior to screening. Prior treatment with immunosuppressant therapies (ISTs) was not required for enrollment. However, patients on selected ISTs (i.e., corticosteroids, azathioprine, mycophenolate mofetil, methotrexate, and tacrolimus) were permitted to continue on therapy, with a requirement for stable dosing until they reached Week 106 in the Study. Similar IST use was permitted in the external placebo control group.

ULTOMIRIS was administered intravenously according to the weight-based recommended dosage [see Dosage and Administration (2.3)].

The demographics were similar between the ULTOMIRIS treatment group from Study ALXN1210-NMO-307 and the placebo treatment group from Study ECU-NMO-301 (including age [median of 46.0 years for ULTOMIRIS versus 44.0 years for placebo] and sex [89.7% female for ULTOMIRIS versus 89.4% female for placebo]). The majority of patients were White or Asian. The median time from diagnosis to first dose was 0.9 years for ULTOMIRIS and 2.0 years for placebo. The median annualized relapse rate (ARR) in the last 24 months was 1.4 for ULTOMIRIS versus 1.9 for placebo, and the median number of historical relapses was 2 for ULTOMIRIS versus 4 for placebo. The median baseline EDSS score was 3.3 for ULTOMIRIS versus 4.0 for placebo. At baseline, 48% of patients in the ULTOMIRIS group received concomitant IST, including corticosteroids, versus 72% of subjects in the placebo group.

The primary endpoint of Study ALXN1210-NMO-307 was the time to first adjudicated on-trial relapse as determined by an independent adjudication committee. No adjudicated on-trial relapses were observed in ULTOMIRIS-treated patients during the Primary Treatment Period, representing a statistically significant difference between the ULTOMIRIS and placebo treatment arms in time to first adjudicated on-trial relapse (p < 0.0001). The hazard ratio (95% confidence interval [CI]) for ULTOMIRIS compared with placebo was 0.014 (0.000, 0.103), representing a 98.6% reduction in the risk of relapse (Figure 2). ULTOMIRIS-treated patients experienced similar improvement in time to first adjudicated on-trial relapse with or without concomitant treatment.

Figure 2: Kaplan-Meier Survival Estimates for Time to First Adjudicated On-Trial Relapse in Study ALXN1210-NMO-307 and Comparative Placebo Arm of Study ECU-NMO-301

Note: The placebo group data were collected as part of Study ECU-NMO-301. Patients who did not experience an adjudicated on-trial relapse were censored at the end of the study period. If a patient in the placebo group was followed longer than any of the patients in the Ultomiris group, then that patient was censored at the longest Ultomiris follow-up time.

16 HOW SUPPLIED/STORAGE AND HANDLING

16.1 How Supplied

ULTOMIRIS (ravulizumab-cwvz) injection is translucent, clear to yellowish color solution supplied in one single-dose vial per carton as:

- 300 mg/3 mL (100 mg/mL) (NDC 25682-025-01)
- 1,100 mg/11 mL (100 mg/mL) (NDC 25682-028-01)

16.2 Storage and Handling

Store ULTOMIRIS vials refrigerated at 2°C - 8°C (36°F - 46°F) in the original carton to protect from light. Do not freeze. Do not shake.

Refer to Dosage and Administration (2) for information on the stability and storage of diluted solutions of ULTOMIRIS.

17 PATIENT COUNSELING INFORMATION

Advise the patients and/or caregivers to read the FDA-approved patient labeling (Medication Guide).

Serious Meningococcal Infections

Advise patients of the risk of serious meningococcal infection. Inform patients of the need to complete or update their meningococcal vaccinations at least 2 weeks prior to receiving the first dose of ULTOMIRIS or receive antibacterial drug prophylaxis if ULTOMIRIS treatment must be initiated immediately and they have not been previously vaccinated. Inform patients of the requirement to be revaccinated according to current ACIP recommendations for meningococcal infection while on ULTOMIRIS therapy [see Warnings and Precautions (5.1)].

Inform patients that vaccination may not prevent serious meningococcal infection and to seek immediate medical attention if the following signs or symptoms occur [see Warnings and Precautions (5.1)]:

- fever
- fever and a rash
- headache with nausea or vomiting
- fever with high heart rate
- headache and a fever
- headache with a stiff neck or stiff back
- confusion
- muscle aches with flu-like symptoms
- eyes sensitive to light

Inform patients that they will be given a Patient Safety Card for ULTOMIRIS that they should carry with them at all times during and for 8 months following treatment with ULTOMIRIS. This card describes symptoms which, if experienced, should prompt the patient to immediately seek medical evaluation.

ULTOMIRIS and SOLIRIS REMS

ULTOMIRIS is available only through a restricted program called ULTOMIRIS and SOLIRIS REMS [see Warnings and Precautions (5.2)].

Inform the patient of the following notable requirements:

- Patients must receive counseling about the risk of serious meningococcal infections.
- Patients must receive written educational materials about this risk.
- Patients must be instructed to carry the Patient Safety Card with them at all times during and for 8 months following treatment with ULTOMIRIS.
- Patients must be instructed to complete or update meningococcal vaccines for serogroups A, C, W, Y and B per ACIP recommendations as directed by the prescriber prior to treatment with ULTOMIRIS.
- Patients must receive antibiotics as directed by the prescriber if they are not up to date with meningococcal vaccines and have to start ULTOMIRIS right away.

Other Infections

Counsel patients of the increased risk of infections, particularly those due to encapsulated bacteria, especially Neisseria species. Advise patients of the need for vaccination against meningococcal infections according to current medical guidelines. Counsel patients about gonorrhea prevention and advise regular testing for patients at risk. Advise patients to report any new signs and symptoms of infection.

Discontinuation

Inform patients with PNH or aHUS that they may develop serious hemolysis or TMA, respectively, when ULTOMIRIS is discontinued and that they will be monitored by their healthcare professional for at least 16 weeks for PNH or at least 12 months for aHUS following ULTOMIRIS discontinuation [see Warnings and Precautions (5.4)].

Inform patients who discontinue ULTOMIRIS to keep the Patient Safety Card with them for 8 months after the last ULTOMIRIS dose, because the increased risk of meningococcal infection persists for several months following discontinuation of ULTOMIRIS.

Infusion-Related Reactions

Advise patients that administration of ULTOMIRIS may result in infusion-related reactions [see Warnings and Precautions (5.6)].

Pregnancy Exposure Registry

There is a pregnancy exposure registry that monitors pregnancy outcomes in women exposed to ULTOMIRIS during pregnancy. Encourage participation and advise patients about how they may enroll in the registry [see Use in Specific Populations (8.1)].

Manufactured by:

Alexion Pharmaceuticals, Inc.
121 Seaport Boulevard
Boston, MA 02210 USA

US License Number 1743

This product, or its use, may be covered by one or more US patents, including US Patent No. 9,079,949; 9,107,861; 9,206,251; 9,371,377; 9,663,574; 9,803,007; 10,227,400; 10,584,164; and 11,365,241 in addition to others including patents pending.

ULTOMIRIS is a registered trademark of Alexion Pharmaceuticals, Inc.

© 2025 Alexion Pharmaceuticals, Inc.

MEDICATION GUIDE
ULTOMIRIS® (ul-toe-meer-is)
(ravulizumab-cwvz)
injection, for intravenous use

What is the most important information I should know about ULTOMIRIS?
ULTOMIRIS is a medicine that affects your immune system. ULTOMIRIS may lower the ability of your immune system to fight infections.

- ULTOMIRIS increases your chance of getting serious meningococcal infections caused by Neisseria meningitidis bacteria. Meningococcal infections may quickly become life-threatening or cause death if not recognized and treated early.
  - You must complete or update your meningococcal vaccine(s) at least 2 weeks before your first dose of ULTOMIRIS.
  - If you have not completed your meningococcal vaccines and ULTOMIRIS must be started right away, you should receive the required vaccine(s) as soon as possible.
  - If you have not been vaccinated and ULTOMIRIS must be started right away, you should also receive antibiotics to take for as long as your healthcare provider tells you.
  - If you had a meningococcal vaccine in the past, you might need additional vaccines before starting ULTOMIRIS. Your healthcare provider will decide if you need additional meningococcal vaccines.
  - Meningococcal vaccines do not prevent all meningococcal infections. Call your healthcare provider or get emergency medical care right away if you get any of these signs and symptoms of a serious meningococcal infection:

- fever
- fever with high heart rate
- headache and fever
- confusion
- muscle aches with flu-like symptoms

- fever and a rash
- headache with nausea or vomiting
- headache with stiff neck or stiff back
- eyes sensitive to light

Your healthcare provider will give you a Patient Safety Card about the risk of serious meningococcal infection. Carry it with you at all times during treatment and for 8 months after your last dose of ULTOMIRIS. Your risk of meningococcal infection may continue for several months after your last dose of ULTOMIRIS. It is important to show this card to any healthcare provider who treats you. This will help them diagnose and treat you quickly.

ULTOMIRIS is only available through a program called the ULTOMIRIS and SOLIRIS Risk Evaluation and Mitigation Strategy (REMS). Before you can receive ULTOMIRIS, your healthcare provider must:

- enroll in the ULTOMIRIS and SOLIRIS REMS program
- counsel you about the risk of serious meningococcal infections
- give you information about the signs and symptoms of serious meningococcal infection
- make sure that you are vaccinated against serious infections caused by meningococcal bacteria and that you receive antibiotics if you need to start ULTOMIRIS right away and you are not up to date on your vaccines
- give you a Patient Safety Card about your risk of meningococcal infection, as discussed above

ULTOMIRIS may also increase the risk of other types of serious infections caused by encapsulated bacteria, including Streptococcus pneumoniae, Haemophilus influenzae, and Neisseria gonorrhoeae.

- If your child is treated with ULTOMIRIS, your child should receive vaccines against Streptococcus pneumoniae and Haemophilus influenzae type b (Hib).
- Certain people may be at risk of serious infections with gonorrhea. Talk to your healthcare provider about whether you are at risk for gonorrhea infection, about gonorrhea prevention, and regular testing.

For more information about side effects, see "What are the possible side effects of ULTOMIRIS?"

What is ULTOMIRIS?

ULTOMIRIS is a prescription medicine called a monoclonal antibody. ULTOMIRIS is used to treat:

- adults and children 1 month of age and older with a disease called Paroxysmal Nocturnal Hemoglobinuria (PNH).
- adults and children 1 month of age and older with a disease called atypical Hemolytic Uremic Syndrome (aHUS).
  ULTOMIRIS is not used in treating people with Shiga toxin E. coli related hemolytic uremic syndrome (STEC-HUS).
- adults with a disease called generalized Myasthenia Gravis (gMG) who are anti-acetylcholine receptor (AChR) antibody-positive.
- adults with a disease called Neuromyelitis Optica Spectrum Disorder (NMOSD) who are anti-aquaporin-4 (AQP4) antibody positive.

It is not known if ULTOMIRIS is safe and effective in children younger than 1 month of age.
It is not known if ULTOMIRIS is safe and effective for the treatment of gMG or NMOSD in children.

Who should not receive ULTOMIRIS?
Do not receive ULTOMIRIS if you have a serious meningococcal infection when you are starting ULTOMIRIS treatment.

Before you receive ULTOMIRIS, tell your healthcare provider about all of your medical conditions, including if you:

- have an infection or fever.
- are pregnant or plan to become pregnant. It is not known if ULTOMIRIS will harm your unborn baby.
  - Pregnancy Registry: There is a registry for pregnant women who take ULTOMIRIS. The purpose of this registry is to check the health of the pregnant mother and her baby. If you are pregnant or become pregnant while taking ULTOMIRIS, talk to your healthcare provider about how you can join this pregnancy registry or you may contact the registry at 1-833-793-0563 or www.UltomirisPregnancyStudy.com to enroll.
- are breastfeeding or plan to breastfeed. It is not known if ULTOMIRIS passes into your breast milk. You should not breastfeed during treatment and for 8 months after your final dose of ULTOMIRIS.

Tell your healthcare provider about all the medicines you take, including prescription and over-the-counter medicines, vitamins, and herbal supplements. ULTOMIRIS and other medicines can affect each other causing side effects.
Know the medicines you take and the vaccines you receive. Keep a list of them to show your healthcare provider and pharmacist when you get a new medicine.

How should I receive ULTOMIRIS?

- Your healthcare provider will decide how long you need to receive ULTOMIRIS for your PNH, your aHUS, your gMG, or your NMOSD.

Adults with PNH, aHUS, gMG, or NMOSD when administered intravenously (by vein)

- You will be given intravenous ULTOMIRIS infusion by a healthcare provider through a needle placed in a vein
- You will usually receive:
  - a starting dose of intravenous ULTOMIRIS infusion by your healthcare provider, and then
  - 2 weeks later, you will start to receive an infusion of ULTOMIRIS every 8 weeks.

Children 1 month of age and older with PNH or aHUS when administered intravenously (by vein)

Your child will be given intravenous ULTOMIRIS infusion by a healthcare provider through a needle placed in a vein

- Your child will usually receive:
  - a starting dose of intravenous ULTOMIRIS infusion by your healthcare provider, and then
  - your healthcare provider will decide how often your child will receive their intravenous ULTOMIRIS infusion, either every 4 weeks or every 8 weeks, depending on their weight, starting 2 weeks after the starting dose.

If you are changing treatment from SOLIRIS to ULTOMIRIS, you should receive your starting dose of ULTOMIRIS at time of your next scheduled dose of SOLIRIS.

- After each administration, you should monitor for infusion-related reactions for at least 1 hour. See "What are the possible side effects of ULTOMIRIS?"
- If you have PNH and you stop receiving ULTOMIRIS, your healthcare provider will need to monitor you closely for at least 16 weeks after you stop ULTOMIRIS. Stopping ULTOMIRIS may cause breakdown of your red blood cells due to PNH.
  Symptoms or problems that can happen due to red blood cell breakdown include:

- drop in your red blood cell count
- tiredness
- blood in your urine
- stomach-area (abdomen) pain

- shortness of breath
- blood clots
- trouble swallowing
- erectile dysfunction (ED) in males

- If you have aHUS, your healthcare provider will need to monitor you closely for at least 12 months after stopping treatment for signs of worsening aHUS or problems related to a type of abnormal clotting and breakdown of your red blood cells called thrombotic microangiopathy (TMA).
  Symptoms or problems that can happen with TMA may include:

- confusion or loss of consciousness
- seizures
- chest pain (angina)

- difficulty breathing
- blood clots or stroke

If you miss an ULTOMIRIS infusion, call your healthcare provider right away.

What are the possible side effects of ULTOMIRIS?

- ULTOMIRIS can cause serious side effects including: See "What is the most important information I should know about ULTOMIRIS?"
- Infusion-related reactions. Infusion-related reactions may happen during your ULTOMIRIS treatment. Symptoms of an infusion-related reaction with ULTOMIRIS may include lower back pain, stomach (abdominal) pain, muscle spasms, changes in blood pressure, tiredness, feeling faint, shaking chills (rigors), discomfort in your arms or legs, or bad taste. Stop treatment of ULTOMIRIS and tell your healthcare provider right away if you develop these symptoms, or any other symptoms during your ULTOMIRIS infusion that may mean you are having a serious infusion-related reaction, including:

- chest pain
- trouble breathing or shortness of breath

- swelling of your face, tongue, or throat
- feel faint or pass out

The most common side effects of ULTOMIRIS in people treated for PNH are:

- upper respiratory tract infection

- headache

The most common side effects of ULTOMIRIS in people treated for aHUS are:

- upper respiratory tract infection
- diarrhea
- nausea
- vomiting

- headache
- high blood pressure
- fever

The most common side effects of ULTOMIRIS in people with gMG are:

- diarrhea

- upper respiratory tract infections

The most common side effects of ULTOMIRIS in people with NMOSD are:

- COVID-19 infection
- headache
- back pain

- urinary tract infection
- joint pain (arthralgia)

Tell your healthcare provider about any side effect that bothers you or that does not go away.
These are not all of the possible side effects of ULTOMIRIS.
Call your doctor for medical advice about side effects. You may report side effects to FDA at 1-800-FDA-1088.

General information about the safe and effective use of ULTOMIRIS.
Medicines are sometimes prescribed for purposes other than those listed in a Medication Guide. You can ask your pharmacist or healthcare provider for information about ULTOMIRIS that is written for health professionals.

What are the ingredients in ULTOMIRIS?

Active ingredient: ravulizumab-cwvz.

Inactive ingredients: L-arginine, polysorbate 80 (vegetable origin), sodium phosphate dibasic, sodium phosphate monobasic, sucrose and Water for Injection.

Manufactured by Alexion Pharmaceuticals, Inc., 121 Seaport Boulevard, Boston, MA 02210 USA.
U.S. License Number 1743
ULTOMIRIS is a registered trademark of Alexion Pharmaceuticals, Inc.
© 2025 Alexion Pharmaceuticals, Inc.
For more information, go to www.ULTOMIRIS.com or call: 1-888-765-4747.

This Medication Guide has been approved by the U.S. Food and Drug Administration.

Revised: 09/2025

PRINCIPAL DISPLAY PANEL - 30 mL Vial Carton

NDC 25682-022-01

ULTOMIRIS®
(ravulizumab-cwvz)
injection

300 mg/30 mL
(10 mg/mL)

For Intravenous Infusion
Dilute with 0.9% Sodium Chloride
Injection prior to use.

Rx only
30 mL Single-dose vial
Discard Unused Portion

ATTENTION: Dispense the enclosed
Medication Guide to each patient

PRINCIPAL DISPLAY PANEL - 3 mL Vial Carton

Rx only

NDC 25682-025-01

ULTOMIRIS®
(ravulizumab-cwvz)
Injection

300 mg/3 mL
(100 mg/mL)

For Intravenous Infusion
Dilute with 0.9% Sodium Chloride
Injection prior to use.
3 mL Single-dose vial
Discard Unused Portion

ATTENTION: Dispense the
enclosed Medication Guide to
each patient

PRINCIPAL DISPLAY PANEL - 11 mL Vial Carton

Rx only

NDC 25682-028-01

ULTOMIRIS®
(ravulizumab-cwvz)
Injection

1,100 mg/11mL
(100 mg/mL)

For Intravenous Infusion
Dilute with 0.9% Sodium Chloride
Injection prior to use.
11 mL Single-dose vial
Discard Unused Portion

ATTENTION: Dispense the
enclosed Medication Guide to
each patient.